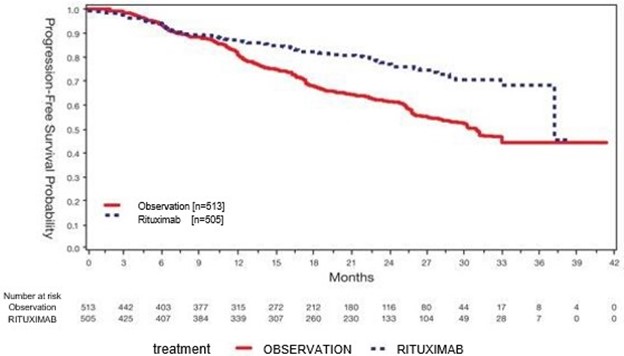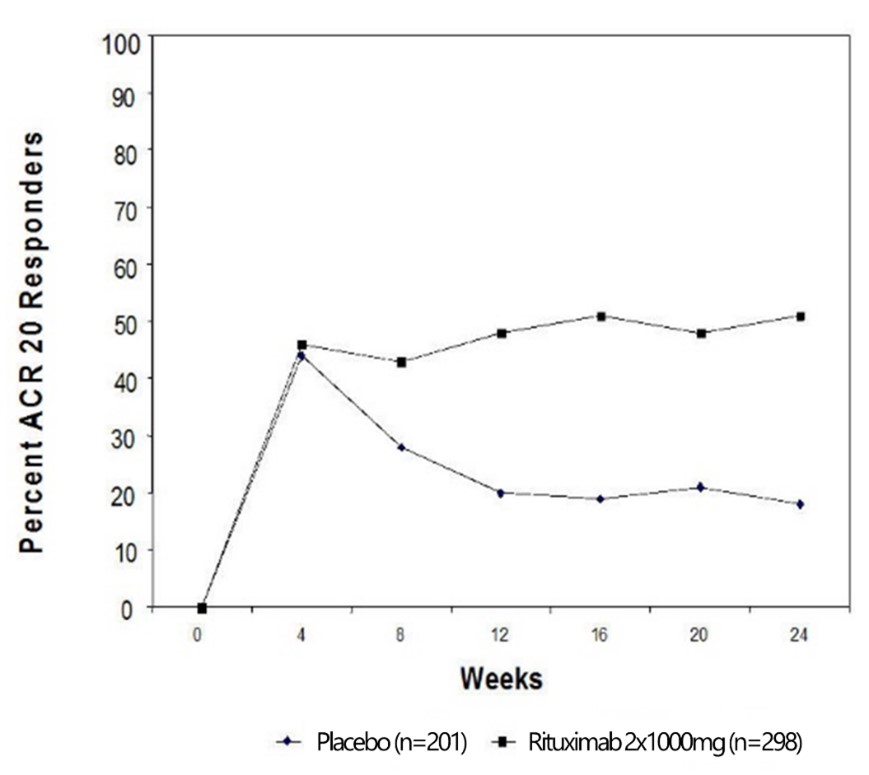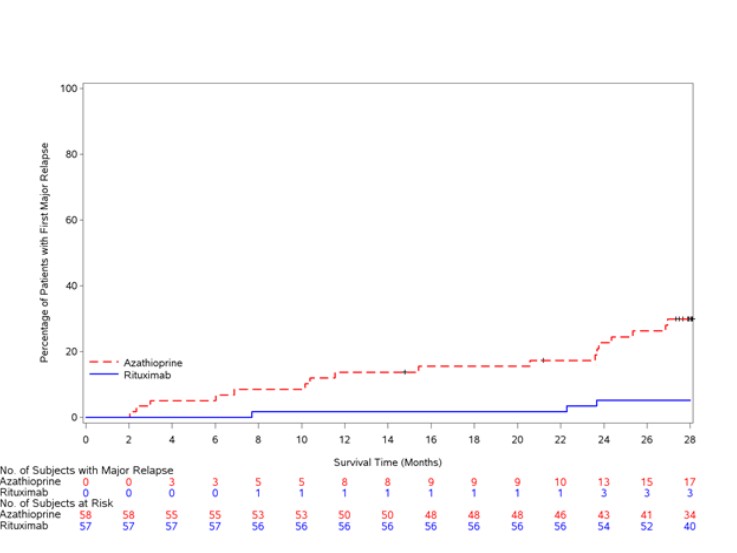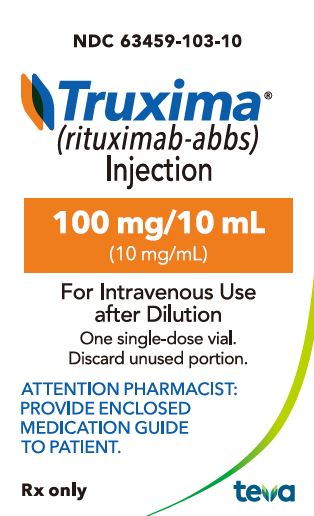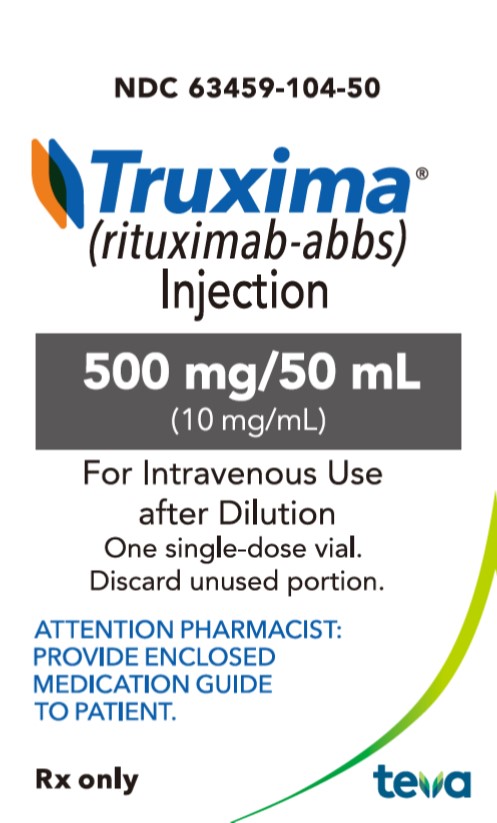 DRUG LABEL: Truxima
NDC: 63459-103 | Form: INJECTION, SOLUTION
Manufacturer: Cephalon, Inc.
Category: prescription | Type: HUMAN PRESCRIPTION DRUG LABEL
Date: 20250618

ACTIVE INGREDIENTS: rituximab 10 mg/1 mL
INACTIVE INGREDIENTS: Sodium Chloride 9 mg/1 mL; Trisodium Citrate Dihydrate 7.35 mg/1 mL; Polysorbate 80 0.7 mg/1 mL; Water

HIGHLIGHTS OF PRESCRIBING INFORMATION

These highlights do not include all the information needed to use TRUXIMA safely and effectively. See full prescribing information for TRUXIMA. TRUXIMA® (rituximab-abbs) injection, for intravenous use
Initial U.S. Approval: 2018
TRUXIMA (rituximab-abbs) is biosimilar to RITUXAN® (rituximab).

WARNING: FATAL INFUSION-RELATED REACTIONS, SEVERE MUCOCUTANEOUS REACTIONS, HEPATITIS B VIRUS REACTIVATION and PROGRESSIVE MULTIFOCAL LEUKOENCEPHALOPATHY (PML)

WARNING: FATAL INFUSION-RELATED REACTIONS, SEVERE MUCOCUTANEOUS REACTIONS, HEPATITIS B VIRUS REACTIVATION and PROGRESSIVE MULTIFOCAL LEUKOENCEPHALOPATHY

See full prescribing information for complete boxed warning.

- Fatal infusion-related reactions within 24 hours of rituximab infusion; approximately 80% of fatal reactions occurred with first infusion. Monitor patients and discontinue TRUXIMA infusion for severe reactions (5.1).
- Severe mucocutaneous reactions, some with fatal outcomes (5.2).
- Hepatitis B virus (HBV) reactivation, in some cases resulting in fulminant hepatitis, hepatic failure, and death (5.3).
- Progressive multifocal leukoencephalopathy (PML) resulting in death (5.4).

RECENT MAJOR CHANGES

Indications and Usage, Pemphigus Vulgaris (1.5) 06/2025

Dosage and Administration (2.7, 2.8) 06/2025

Warnings and Precautions (5.1, 5.12) 06/2025

1 INDICATIONS AND USAGE

TRUXIMA (rituximab-abbs) is a CD20-directed cytolytic antibody indicated for the treatment of adult patients with:

- Non-Hodgkin's Lymphoma (NHL) (1.1).
  - Relapsed or refractory, low grade or follicular, CD20-positive B-cell NHL as a single agent.
  - Previously untreated follicular, CD20-positive, B-cell NHL in combination with first line chemotherapy and, in patients achieving a complete or partial response to a rituximab product in combination with chemotherapy, as single-agent maintenance therapy.
  - Non-progressing (including stable disease), low-grade, CD20-positive, B-cell NHL as a single agent after first-line cyclophosphamide, vincristine, and prednisone (CVP) chemotherapy.
  - Previously untreated diffuse large B-cell, CD20-positive NHL in combination with (cyclophosphamide, doxorubicin, vincristine, and prednisone) (CHOP) or other anthracycline-based chemotherapy regimens.

- Chronic Lymphocytic Leukemia (CLL) (1.2).
  - Previously untreated and previously treated CD20-positive CLL in combination with fludarabine and cyclophosphamide (FC).
- Rheumatoid Arthritis (RA) in combination with methotrexate in adult patients with moderately-to severely-active RA who have inadequate response to one or more TNF antagonist therapies (1.3).
- Granulomatosis with Polyangiitis (GPA) (Wegener’s Granulomatosis) and Microscopic Polyangiitis (MPA) in adult patients in combination with glucocorticoids (1.4).
- Moderate to severe Pemphigus Vulgaris (PV) in adult patients (1.5)

2 DOSAGE AND ADMINISTRATION

- Administer only as an intravenous infusion (2.1).
- Do not administer as an intravenous push or bolus (2.1).
- TRUXIMA should only be administered by a healthcare professional with appropriate medical support to manage severe infusion-related reactions that can be fatal if they occur(2.1).
- The dose for NHL is 375 mg/m^2 (2.2).
- The dose for CLL is 375 mg/m^2 in the first cycle and 500 mg/m^2 in cycles 2-6, in combination with FC, administered every 28 days (2.3).
- The dose as a component of Zevalin® (ibritumomab tiuxetan) Therapeutic Regimen is 250 mg/m^2 (2.4).
- The dose for RA in combination with methotrexate is two-1000 mg intravenous infusions separated by 2 weeks (one course) every 24 weeks or based on clinical evaluation, but not sooner than every 16 weeks. Methylprednisolone 100 mg intravenous or equivalent glucocorticoid is recommended 30 minutes prior to each infusion (2.5).
- The induction dose for adult patients with active GPA and MPA in combination with glucocorticoids is 375 mg/m2 once weekly for 4 weeks. The follow up dose for adult patients with GPA and MPA who have achieved disease control with induction treatment, in combination with glucocorticoids is two 500 mg intravenous infusions separated by two weeks, followed by a 500 mg intravenous infusion every 6 months thereafter based on clinical evaluation (2.6).
- The dose for PV is two-1,000 mg intravenous infusions separated by
  2 weeks in combination with a tapering course of glucocorticoids, then a 500 mg intravenous infusion at Month 12 and every 6 months thereafter or based on clinical evaluation. Dose upon relapse is a 1,000 mg intravenous infusion with considerations to resume or increase the glucocorticoid dose based on clinical evaluation. Subsequent infusions may be no sooner than 16 weeks after the previous infusion (2.7). Methylprednisolone 100 mg intravenous or equivalent glucocorticoid is recommended 30 minutes prior to each infusion (2.8).

3 DOSAGE FORMS AND STRENGTHS

Injection: 100 mg/10 mL (10 mg/mL) and 500 mg/50 mL (10 mg/mL) solution in single dose vials.

4 CONTRAINDICATIONS

None (4)

5 WARNINGS AND PRECAUTIONS

- Tumor lysis syndrome: Administer aggressive intravenous hydration, anti-hyperuricemic agents, monitor renal function (5.5).
- Infections: Withhold TRUXIMA and institute appropriate anti-infective therapy (5.6).
- Cardiac adverse reactions: Discontinue infusions in case of serious or life-threatening events (5.7).
- Renal toxicity: Discontinue in patients with rising serum creatinine or oliguria (5.8).
- Bowel obstruction and perforation: Consider and evaluate for abdominal pain, vomiting, or related symptoms (5.9).
- Immunizations: Live virus vaccinations prior to or during TRUXIMA treatment not recommended (5.10).
- Embryo-Fetal toxicity: Can cause fetal harm. Advise females of reproductive potential of the potential risk to a fetus and use of effective contraception (5.11).

6 ADVERSE REACTIONS

Most common adverse reactions in clinical trials were:

- NHL (greater than or equal to 25%): infusion-related reactions, fever, lymphopenia, chills, infection, and asthenia (6.1).
- CLL (greater than or equal to 25%): infusion-related reactions and neutropenia (6.1).
- RA (greater than or equal to 10%): upper respiratory tract infection, nasopharyngitis, urinary tract infection, and bronchitis (other important adverse reactions include infusion-related reactions, serious infections, and cardiovascular events) (6.1).
- GPA and MPA (greater than or equal to 15 %): infections, nausea, diarrhea, headache, muscle spasms, anemia, peripheral edema, infusion-related reactions (6.1).
- PV (greater than or equal to 15%): infusion-related reactions, depression, upper respiratory tract infection/nasopharyngitis, headache (other important adverse reactions include infections) (6.1).

To report SUSPECTED ADVERSE REACTIONS, contact TEVA Pharmaceuticals at 1-888-483-8279 or FDA at 1-800-FDA-1088 or www.fda.gov/medwatch.

7 DRUG INTERACTIONS

Renal toxicity when used in combination with cisplatin (5.8).

8 USE IN SPECIFIC POPULATIONS

- Lactation: Advise not to breastfeed (8.2).
- Geriatric Use: In CLL patients older than 70 years of age, exploratory analyses suggest no benefit with the addition of rituximab to FC (8.5).

FULL PRESCRIBING INFORMATION

WARNING: FATAL INFUSION-RELATED REACTIONS, SEVERE MUCOCUTANEOUS REACTIONS, HEPATITIS B VIRUS REACTIVATION and PROGRESSIVE MULTIFOCAL LEUKOENCEPHALOPATHY (PML)

Infusion-Related Reactions

Administration of rituximab products, including TRUXIMA, can result in serious, including fatal, infusion-related reactions. Deaths within 24 hours of rituximab infusion have occurred. Approximately 80% of fatal infusion-related reactions occurred in association with the first infusion. Monitor patients closely. Discontinue TRUXIMA infusion for severe reactions and provide medical treatment for Grade 3 or 4 infusion-related reactions [see Warnings and Precautions (5.1), Adverse Reactions (6.1)].

Severe Mucocutaneous Reactions

Severe, including fatal, mucocutaneous reactions can occur in patients receiving rituximab products [see Warnings and Precautions (5.2)].

Hepatitis B Virus (HBV) Reactivation

HBV reactivation can occur in patients treated with rituximab products, in some cases resulting in fulminant hepatitis, hepatic failure, and death. Screen all patients for HBV infection before treatment initiation, and monitor patients during and after treatment with TRUXIMA. Discontinue TRUXIMA and concomitant medications in the event of HBV reactivation [see Warnings and Precautions (5.3)].

Progressive Multifocal Leukoencephalopathy (PML), including fatal PML, can occur in patients receiving rituximab products [see Warnings and Precautions (5.4) and Adverse Reactions (6.1)].

1 INDICATIONS AND USAGE

1.1 Non–Hodgkin's Lymphoma (NHL)

TRUXIMA (rituximab-abbs) is indicated for the treatment of adult patients with:

- Relapsed or refractory, low-grade or follicular, CD20-positive, B-cell NHL as a single agent.
- Previously untreated follicular, CD20-positive, B-cell NHL in combination with first line chemotherapy and, in patients achieving a complete or partial response to a rituximab product in combination with chemotherapy, as single-agent maintenance therapy.
- Non-progressing (including stable disease), low-grade, CD20-positive, B-cell NHL as a single agent after first-line cyclophosphamide, vincristine, and prednisone (CVP) chemotherapy.
- Previously untreated diffuse large B-cell, CD20-positive NHL in combination with cyclophosphamide, doxorubicin, vincristine, prednisone (CHOP) or other anthracycline-based chemotherapy regimens.

1.2 Chronic Lymphocytic Leukemia (CLL)

TRUXIMA is indicated, in combination with fludarabine and cyclophosphamide (FC), for the treatment of adult patients with previously untreated and previously treated CD20-positive CLL.

1.3 Rheumatoid Arthritis (RA)

TRUXIMA, in combination with methotrexate, is indicated for the treatment of adult patients with moderately-to-severely-active rheumatoid arthritis who have had an inadequate response to one or more TNF antagonist therapies.

1.4 Granulomatosis with Polyangiitis (GPA) (Wegener’s Granulomatosis) and Microscopic Polyangiitis (MPA)

TRUXIMA, in combination with glucocorticoids, is indicated for the treatment of adult patients with Granulomatosis with Polyangiitis (GPA) (Wegener’s Granulomatosis) and Microscopic Polyangiitis (MPA).

1.5 Pemphigus Vulgaris (PV)

TRUXIMA is indicated for the treatment of adult patients with moderate to severe pemphigus vulgaris.

2 DOSAGE AND ADMINISTRATION

2.1 Important Dosing Information

Administer only as an Intravenous Infusion [see Dosage and Administration (2.8)].

Do not administer as an intravenous push or bolus. TRUXIMA should only be administered by a healthcare professional with appropriate medical support to manage severe infusion-related reactions that can be fatal if they occur [see Warnings and Precautions (5.1)].

Premedicate before each infusion [see Dosage and Administration (2.8)].

Prior to First Infusion: Screen all patients for HBV infection by measuring HBsAg and anti-HBc before initiating treatment with TRUXIMA [see Warnings and Precautions (5.3)]. Obtain complete blood counts (CBC) including platelets prior to the first dose.

During TRUXIMA Therapy: In patients with lymphoid malignancies, during treatment with TRUXIMA monotherapy, obtain complete blood counts (CBC) with differential and platelet counts prior to each TRUXIMA course. During treatment with TRUXIMA and chemotherapy, obtain CBC with differential and platelet counts at weekly to monthly intervals and more frequently in patients who develop cytopenias [see Adverse Reactions (6.1)]. In patients with RA, GPA or MPA, obtain CBC with differential and platelet counts at two to four month intervals during TRUXIMA therapy. Continue to monitor for cytopenias after final dose and until resolution.

- First Infusion:
  Initiate infusion at a rate of 50 mg/hr. In the absence of infusion toxicity, increase infusion rate by 50 mg/hr increments every 30 minutes, to a maximum of 400 mg/hr.
- Subsequent Infusions:
  Standard Infusion: Initiate infusion at a rate of 100 mg/hr. In the absence of infusion toxicity, increase rate by 100 mg/hr increments at 30-minute intervals, to a maximum of 400 mg/hr.

For previously untreated follicular NHL and DLBCL patients:

If patients did not experience a Grade 3 or 4 infusion related adverse event during Cycle 1, a 90-minute infusion can be administered in Cycle 2 with a glucocorticoid-containing chemotherapy regimen.

Initiate at a rate of 20% of the total dose given in the first 30 minutes and the remaining 80% of the total dose given over the next 60 minutes. If the 90-minute infusion is tolerated in Cycle 2, the same rate can be used when administering the remainder of the treatment regimen (through Cycle 6 or 8).

Patients who have clinically significant cardiovascular disease or who have a circulating lymphocyte count ≥5000/mm^3 before Cycle 2 should not be administered the 90-minute infusion [see Clinical Studies (14.4)].

- Interrupt the infusion or slow the infusion rate for infusion-related reactions [see Boxed Warning, Warnings and Precautions (5.1)]. Continue the infusion at one-half the previous rate upon improvement of symptoms.

2.2 Recommended Dose for Non-Hodgkin's Lymphoma (NHL)

The recommended dose is 375 mg/m^2 as an intravenous infusion according to the following schedules:

- Relapsed or Refractory, Low-Grade or Follicular, CD20-Positive, B-Cell NHL
  Administer once weekly for 4 or 8 doses.
- Retreatment for Relapsed or Refractory, Low-Grade or Follicular, CD20-Positive, B-Cell NHL
  Administer once weekly for 4 doses.
- Previously Untreated, Follicular, CD20-Positive, B-Cell NHL
  Administer on Day 1 of each cycle of chemotherapy for up to 8 doses. In patients with complete or partial response, initiate TRUXIMA maintenance eight weeks following completion of a rituximab product in combination with chemotherapy. Administer TRUXIMA as a single-agent every 8 weeks for 12 doses.
- Non-progressing, Low-Grade, CD20-Positive, B-Cell NHL, after first-line CVP chemotherapy
  Following completion of 6–8 cycles of CVP chemotherapy, administer once weekly for 4 doses at 6-month intervals to a maximum of 16 doses.
- Diffuse Large B-Cell NHL
  Administer on Day 1 of each cycle of chemotherapy for up to 8 infusions.

2.3 Recommended Dose for Chronic Lymphocytic Leukemia (CLL)

The recommended dose is:

- 375 mg/m^2 the day prior to the initiation of FC chemotherapy, then 500 mg/m^2 on Day 1 of cycles 2-6 (every 28 days).

2.4 Recommended Dose as a Component of Zevalin® for treatment of NHL

- When used as part of the Zevalin therapeutic regimen, infuse 250 mg/m^2 in accordance with the Zevalin package insert. Refer to the Zevalin package insert for full prescribing information regarding the Zevalin therapeutic regimen.

2.5 Recommended Dose for Rheumatoid Arthritis (RA)

- Administer TRUXIMA as two-1000 mg intravenous infusions separated by 2 weeks.
- Glucocorticoids administered as methylprednisolone 100 mg intravenous or its equivalent 30 minutes prior to each infusion are recommended to reduce the incidence and severity of infusion-related reactions.
- Subsequent courses should be administered every 24 weeks or based on clinical evaluation, but not sooner than every 16 weeks.
- TRUXIMA is given in combination with methotrexate.

2.6 Recommended Dose for Granulomatosis with Polyangiitis (GPA) (Wegener’s Granulomatosis) and Microscopic Polyangiitis (MPA)

Induction Treatment of Adult Patients with Active GPA/MPA

- Administer TRUXIMA as a 375 mg/m2 intravenous infusion once weekly for 4 weeks for patients with active GPA or MPA.
- Glucocorticoids administered as methylprednisolone 1000 mg intravenously per day for 1 to 3 days followed by oral prednisone as per clinical practice. This regimen should begin within 14 days prior to or with the initiation of TRUXIMA and may continue during and after the 4 week induction course of TRUXIMA treatment.

Follow up Treatment of Adult Patients with GPA/MPA who have achieved disease control with induction treatment

- Administer TRUXIMA as two 500 mg intravenous infusions separated by two weeks, followed by a 500 mg intravenous infusion every 6 months thereafter based on clinical evaluation.
- If induction treatment of active disease was with a rituximab product, initiate follow up treatment with TRUXIMA within 24 weeks after the last induction infusion with a rituximab product or based on clinical evaluation, but no sooner than 16 weeks after the last induction infusion with a rituximab product.
- If induction treatment of active disease was with other standard of care immunosuppressants, initiate TRUXIMA follow up treatment within the 4 week period that follows achievement of disease control.

2.7 Recommended Dose for Pemphigus Vulgaris (PV)

- Administer TRUXIMA as two-1,000 mg intravenous infusions separated by 2 weeks in combination with a tapering course of glucocorticoids.
- Maintenance treatmentAdminister TRUXIMA as a 500 mg intravenous infusion at Month 12 and every 6 months thereafter or based on clinical evaluation.

- Treatment of relapseAdminister TRUXIMA as a 1,000 mg intravenous infusion on relapse, and consider resuming or increasing the glucocorticoid dose based on clinical evaluation.

Subsequent infusions of TRUXIMA may be administered no sooner than 16 weeks following the previous infusion.

2.8 Recommended Dose for Premedication and Prophylactic Medications

Premedicate with acetaminophen and an antihistamine before each infusion of TRUXIMA. For patients administered TRUXIMA according to the 90-minute infusion rate, the glucocorticoid component of their chemotherapy regimen should be administered prior to infusion [see Clinical Studies (14.4)].

For RA, GPA and MPA patients, methylprednisolone 100 mg intravenously or its equivalent is recommended 30 minutes prior to each infusion.

Provide prophylaxis treatment for Pneumocystis jirovecii pneumonia (PCP) and herpes virus infections for patients with CLL during treatment and for up to 12 months following treatment as appropriate [see Warnings and Precautions (5.6)].

PCP prophylaxis is also recommended for patients with GPA and MPA during treatment and for at least 6 months following the last TRUXIMA infusion.

2.9 Administration and Storage

- Use appropriate aseptic technique. Parenteral drug products should be inspected visually for particulate matter and discoloration prior to administration. TRUXIMA should be a clear to opalescent, colorless to pale yellow solution. Do not use vial if particulates or discoloration is present.

Administration

Use a sterile needle and syringe to prepare TRUXIMA. Withdraw the necessary amount of TRUXIMA and dilute to a final concentration of 1 mg/mL to 4 mg/mL in an infusion bag containing either 0.9% Sodium Chloride, USP, or 5% Dextrose Injection, USP. Gently invert the bag to mix the solution. Do not mix or dilute with other drugs. Discard any unused portion left in the vial

Storage

Diluted TRUXIMA solutions for infusion may be stored at 2°C to 8°C (36°F to 46°F) for 24 hours.

Diluted TRUXIMA solutions for infusion have been shown to be stable for an additional 24 hours at room temperature. However, since TRUXIMA solutions do not contain a preservative, diluted solutions should be stored refrigerated (2°C to 8°C). No incompatibilities between TRUXIMA and polyvinylchloride or polyethylene bags have been observed.

3 DOSAGE FORMS AND STRENGTHS

Injection: TRUXIMA is a clear to opalescent, colorless to pale yellow solution for intravenous infusion:

- 100 mg/10 mL (10 mg/mL) in a single-dose vial
- 500 mg/50 mL (10 mg/mL) in a single-dose vial

4 CONTRAINDICATIONS

None.

5 WARNINGS AND PRECAUTIONS

5.1 Infusion-Related Reactions

Rituximab products can cause severe, including fatal, infusion-related reactions. Severe reactions typically occurred during the first infusion with time to onset of 30 to 120 minutes. Rituximab product-induced infusion-related reactions and sequelae include urticaria, hypotension, angioedema, hypoxia, bronchospasm, pulmonary infiltrates, acute respiratory distress syndrome, myocardial infarction, ventricular fibrillation, cardiogenic shock, anaphylactoid events, or death.

Premedicate patients with an antihistamine and acetaminophen prior to dosing. For RA, GPA and MPA, and PV patients, methylprednisolone 100 mg intravenously or its equivalent is recommended 30 minutes prior to each infusion. Institute medical management (e.g., glucocorticoids, epinephrine, bronchodilators, or oxygen) for infusion-related reactions as needed. Depending on the severity of the infusion-related reaction and the required interventions, temporarily or permanently discontinue TRUXIMA. Resume infusion at a minimum 50% reduction in rate after symptoms have resolved. Closely monitor the following patients: those with pre-existing cardiac or pulmonary conditions, those who experienced prior cardiopulmonary adverse reactions, and those with high numbers of circulating malignant cells (greater than or equal to 25,000/mm3) [see Warnings and Precautions (5.7), Adverse Reactions (6.1)].

5.2 Severe Mucocutaneous Reactions

Mucocutaneous reactions, some with fatal outcome, can occur in patients treated with rituximab products. These reactions include paraneoplastic pemphigus, Stevens-Johnson syndrome, lichenoid dermatitis, vesiculobullous dermatitis, and toxic epidermal necrolysis. The onset of these reactions has been variable and includes reports with onset on the first day of rituximab exposure. Discontinue TRUXIMA in patients who experience a severe mucocutaneous reaction. The safety of re-administration of rituximab products to patients with severe mucocutaneous reactions has not been determined.

5.3 Hepatitis B Virus Reactivation (HBV)

Hepatitis B virus (HBV) reactivation, in some cases resulting in fulminant hepatitis, hepatic failure and death, can occur in patients treated with drugs classified as CD20-directed cytolytic antibodies, including rituximab products. Cases have been reported in patients who are hepatitis B surface antigen (HBsAg) positive and also in patients who are HBsAg negative but are hepatitis B core antibody (anti-HBc) positive. Reactivation also has occurred in patients who appear to have resolved hepatitis B infection (i.e., HBsAg negative, anti-HBc positive and hepatitis B surface antibody [anti-HBs] positive).

HBV reactivation is defined as an abrupt increase in HBV replication manifesting as a rapid increase in serum HBV DNA levels or detection of HBsAg in a person who was previously HBsAg negative and anti-HBc positive. Reactivation of HBV replication is often followed by hepatitis, i.e., increase in transaminase levels. In severe cases increase in bilirubin levels, liver failure, and death can occur.

Screen all patients for HBV infection by measuring HBsAg and anti-HBc before initiating treatment with TRUXIMA. For patients who show evidence of prior hepatitis B infection (HBsAg positive [regardless of antibody status] or HBsAg negative but anti-HBc positive), consult with physicians with expertise in managing hepatitis B regarding monitoring and consideration for HBV antiviral therapy before and/or during TRUXIMA treatment.

Monitor patients with evidence of current or prior HBV infection for clinical and laboratory signs of hepatitis or HBV reactivation during and for several months following rituximab therapy. HBV reactivation has been reported up to 24 months following completion of TRUXIMA therapy.

In patients who develop reactivation of HBV while on TRUXIMA, immediately discontinue TRUXIMA and any concomitant chemotherapy, and institute appropriate treatment. Insufficient data exist regarding the safety of resuming TRUXIMA treatment in patients who develop HBV reactivation. Resumption of TRUXIMA treatment in patients whose HBV reactivation resolves should be discussed with physicians with expertise in managing HBV.

5.4 Progressive Multifocal Leukoencephalopathy (PML)

JC virus infection resulting in PML and death can occur in rituximab product-treated patients with hematologic malignancies or with autoimmune diseases. The majority of patients with hematologic malignancies diagnosed with PML received rituximab in combination with chemotherapy or as part of a hematopoietic stem cell transplant. The patients with autoimmune diseases had prior or concurrent immunosuppressive therapy. Most cases of PML were diagnosed within 12 months of their last infusion of rituximab.

Consider the diagnosis of PML in any patient presenting with new-onset neurologic manifestations. Evaluation of PML includes, but is not limited to, consultation with a neurologist, brain MRI, and lumbar puncture.

Discontinue TRUXIMA and consider discontinuation or reduction of any concomitant chemotherapy or immunosuppressive therapy in patients who develop PML.

5.5 Tumor Lysis Syndrome (TLS)

Acute renal failure, hyperkalemia, hypocalcemia, hyperuricemia, or hyperphosphatemia from tumor lysis, sometimes fatal, can occur within 12-24 hours after the first infusion of rituximab products in patients with NHL. A high number of circulating malignant cells (≥25,000/mm3) or high tumor burden, confers a greater risk of TLS.
Administer aggressive intravenous hydration and anti-hyperuricemic therapy in patients at high risk for TLS. Correct electrolyte abnormalities, monitor renal function and fluid balance, and administer supportive care, including dialysis as indicated [see Warnings and Precautions (5.8)].

5.6 Infections

Serious, including fatal, bacterial, fungal, and new or reactivated viral infections can occur during and following the completion of rituximab product-based therapy. Infections have been reported in some patients with prolonged hypogammaglobulinemia (defined as hypogammaglobulinemia >11 months after rituximab exposure). New or reactivated viral infections included cytomegalovirus, herpes simplex virus, parvovirus B19, varicella zoster virus, West Nile virus, and hepatitis B and C. Discontinue TRUXIMA for serious infections and institute appropriate anti-infective therapy.[seeAdverse Reactions (6.1, 6.2)]. TRUXIMA is not recommended for use in patients with severe, active infections.

5.7 Cardiovascular Adverse Reactions

Cardiac adverse reactions, including ventricular fibrillation, myocardial infarction, and cardiogenic shock may occur in patients receiving rituximab products. Discontinue infusions for serious or life-threatening cardiac arrhythmias. Perform cardiac monitoring during and after all infusions of TRUXIMA for patients who develop clinically significant arrhythmias, or who have a history of arrhythmia or angina [see Adverse Reactions (6.1)].

5.8 Renal Toxicity

Severe, including fatal, renal toxicity can occur after rituximab product administration in patients with NHL. Renal toxicity has occurred in patients who experience tumor lysis syndrome and in patients with NHL administered concomitant cisplatin therapy during clinical trials. The combination of cisplatin and TRUXIMA is not an approved treatment regimen. Monitor closely for signs of renal failure and discontinue TRUXIMA in patients with a rising serum creatinine or oliguria. [see Warnings and Precautions (5.5)].

5.9 Bowel Obstruction and Perforation

Abdominal pain, bowel obstruction and perforation, in some cases leading to death, can occur in patients receiving rituximab products in combination with chemotherapy. In postmarketing reports, the mean time to documented gastrointestinal perforation was 6 (range 1-77) days in patients with NHL. Evaluate if symptoms of obstruction such as abdominal pain or repeated vomiting occur.

5.10 Immunization

The safety of immunization with live viral vaccines following rituximab product therapy has not been studied and vaccination with live virus vaccines is not recommended before or during treatment.

For patients treated with TRUXIMA, physicians should review the patient’s vaccination status and patients should, if possible, be brought up-to-date with all immunizations in agreement with current immunization guidelines prior to initiating TRUXIMA and administer non live vaccines at least 4 weeks prior to a course of TRUXIMA.

The effect of rituximab on immune responses was assessed in a randomized, controlled study in patients with RA treated with rituximab and methotrexate (MTX) compared to patients treated with MTX alone.

A response to pneumococcal vaccination (a T-cell independent antigen) as measured by an increase in antibody titers to at least 6 of 12 serotypes was lower in patients treated with rituximab plus MTX as compared to patients treated with MTX alone (19% vs. 61%). A lower proportion of patients in the rituximab plus MTX group developed detectable levels of anti-keyhole limpet hemocyanin antibodies (a novel protein antigen) after vaccination compared to patients on MTX alone (47% vs. 93%).

A positive response to tetanus toxoid vaccine (a T-cell dependent antigen with existing immunity) was similar in patients treated with rituximab plus MTX compared to patients on MTX alone (39% vs. 42%). The proportion of patients maintaining a positive Candida skin test (to evaluate delayed type hypersensitivity) was also similar (77% of patients on rituximab plus MTX vs. 70% of patients on MTX alone).

Most patients in the rituximab-treated group had B-cell counts below the lower limit of normal at the time of immunization. The clinical implications of these findings are not known.

5.11 Embryo-Fetal Toxicity

Based on human data, rituximab products can cause fetal harm due to B-cell lymphocytopenia in infants exposed in-utero. Advise pregnant women of the potential risk to a fetus. Advise females of reproductive potential to use effective contraception while receiving TRUXIMA and for at least 12 months after the last dose [see Use in Specific Populations (8.1, 8.3)].

5.12 Concomitant Use with Other Biologic Agents and DMARDS other than Methotrexate in RA, GPA and MPA

Limited data are available on the safety of the use of biologic agents or disease modifying antirheumatic drugs (DMARDs) other than methotrexate in RA patients exhibiting peripheral B-cell depletion following treatment with rituximab. Observe patients closely for signs of infection if biologic agents and/or DMARDs are used concomitantly. Use of concomitant immunosuppressants other than corticosteroids has not been studied in GPA or MPA, or PV patients exhibiting peripheral B-cell depletion following treatment with rituximab products.

5.13 Use in RA Patients Who Have Not Had Prior Inadequate Response to Tumor Necrosis Factor (TNF) Antagonists

While the efficacy of rituximab was supported in four controlled trials in patients with RA with prior inadequate responses to non-biologic DMARDs, and in a controlled trial in MTX-naïve patients, a favorable risk-benefit relationship has not been established in these populations. The use of TRUXIMA in patients with RA who have not had prior inadequate response to one or more TNF antagonists is not recommended [see Clinical Studies (14.6)].

6 ADVERSE REACTIONS

The following clinically significant adverse reactions are discussed in greater detail in other sections of the labeling:

- Infusion-related reactions [see Warnings and Precautions (5.1)]
- Severe mucocutaneous reactions [see Warnings and Precautions (5.2)]
- Hepatitis B reactivation with fulminant hepatitis [see Warnings and Precautions (5.3)]
- Progressive multifocal leukoencephalopathy [see Warnings and Precautions (5.4)]
- Tumor lysis syndrome [see Warnings and Precautions (5.5)]
- Infections [see Warnings and Precautions (5.6)]
- Cardiovascular adverse reactions [see Warnings and Precautions (5.7)]
- Renal toxicity [see Warnings and Precautions (5.8)]
- Bowel obstruction and perforation [see Warnings and Precautions (5.9)]

6.1 Clinical Trials Experience in Lymphoid Malignancies

Because clinical trials are conducted under widely varying conditions, adverse reaction rates observed in the clinical trials of a drug cannot be directly compared to rates in the clinical trials of another drug and may not reflect the rates observed in clinical practice.

B-Cell Malignancies

The data described below reflect exposure to rituximab in 3,092 patients, with exposures ranging from a single infusion up to 2 years. Rituximab was studied in both single-arm and controlled trials (n=356 and n=2,427). The population included 1180 patients with low grade or follicular lymphoma, 927 patients with DLBCL, 676 patients with CLL, and 309 patients with another indication. Most NHL patients received rituximab as an infusion of 375 mg/m^2 per infusion, given as a single agent weekly for up to 8 doses, in combination with chemotherapy for up to 8 doses, or following chemotherapy for up to 16 doses. CLL patients received rituximab 375 mg/m^2 as an initial infusion followed by 500 mg/m^2 for up to 5 doses, in combination with fludarabine and cyclophosphamide. Seventy-one percent of CLL patients received 6 cycles and 90% received at least 3 cycles of rituximab-based therapy.

The most common adverse reactions of rituximab (incidence ≥25%) observed in clinical trials of patients with NHL were infusion-related reactions, fever, lymphopenia, chills, infection, and asthenia.

The most common adverse reactions of rituximab (incidence ≥25%) observed in clinical trials of patients with CLL were: infusion-related reactions and neutropenia.

Infusion-Related Reactions

In the majority of patients with NHL, infusion-related reactions consisting of fever, chills/rigors, nausea, pruritus, angioedema, hypotension, headache, bronchospasm, urticaria, rash, vomiting, myalgia, dizziness, or hypertension occurred during the first rituximab infusion. Infusion-related reactions typically occurred within 30 to 120 minutes of beginning the first infusion and resolved with slowing or interruption of the rituximab infusion and with supportive care (diphenhydramine, acetaminophen, and intravenous saline). The incidence of infusion-related reactions was highest during the first infusion (77%) and decreased with each subsequent infusion. [see Warnings and Precautions (5.1)]. In patients with previously untreated follicular NHL or previously untreated DLBCL, who did not experience a Grade 3 or 4 infusion-related reaction in Cycle 1 and received a 90-minute infusion of rituximab at Cycle 2, the incidence of Grade 3-4 infusion-related reactions on the day of, or day after the infusion was 1.1% (95% CI [0.3%, 2.8%]). For Cycles 2-8, the incidence of Grade 3-4 infusion-related reactions on the day of or day after the 90-minute infusion, was 2.8% (95% CI [1.3%, 5.0%]) [see Warnings and Precautions (5.1), Clinical Studies (14.4)].

Infections

Serious infections (NCI CTCAE Grade 3 or 4), including sepsis, occurred in less than 5% of patients with NHL in the single-arm studies. The overall incidence of infections was 31% (bacterial 19%, viral 10%, unknown 6%, and fungal 1%) [see Warnings and Precautions (5.6)].

In randomized, controlled studies where rituximab was administered following chemotherapy for the treatment of follicular or low-grade NHL, the rate of infection was higher among patients who received rituximab. In diffuse large B-cell lymphoma patients, viral infections occurred more frequently in those who received rituximab.

Cytopenias and hypogammaglobulinemia

In patients with NHL receiving rituximab monotherapy, NCI-CTC Grade 3 and 4 cytopenias were reported in 48% of patients. These included lymphopenia (40%), neutropenia (6%), leukopenia (4%), anemia (3%), and thrombocytopenia (2%). The median duration of lymphopenia was 14 days (range, 1-588 days) and of neutropenia was 13 days (range, 2-116 days). A single occurrence of transient aplastic anemia (pure red cell aplasia) and two occurrences of hemolytic anemia following rituximab therapy occurred during the single-arm studies.

In studies of monotherapy, rituximab -induced B-cell depletion occurred in 70% to 80% of patients with NHL. Decreased IgM and IgG serum levels occurred in 14% of these patients.

In CLL trials, the frequency of prolonged neutropenia and late-onset neutropenia was higher in patients treated with R-FC compared to patients treated with FC. Prolonged neutropenia is defined as Grade 3-4 neutropenia that has not resolved between 24 and 42 days after the last dose of study treatment. Late-onset neutropenia is defined as Grade 3-4 neutropenia starting at least 42 days after the last treatment dose.

In patients with previously untreated CLL, the frequency of prolonged neutropenia was 8.5% for patients who received R-FC (n=402) and 5.8% for patients who received FC (n=398). In patients who did not have prolonged neutropenia, the frequency of late-onset neutropenia was 14.8% of 209 patients who received R-FC and 4.3% of 230 patients who received FC.

For patients with previously treated CLL, the frequency of prolonged neutropenia was 24.8% for patients who received R-FC (n=274) and 19.1% for patients who received FC (n=274). In patients who did not have prolonged neutropenia, the frequency of late-onset neutropenia was 38.7% in 160 patients who received R-FC and 13.6% of 147 patients who received FC.

Relapsed or Refractory, Low-Grade NHL

Adverse reactions presented in Table 1 occurred in 356 patients with relapsed or refractory, low-grade or follicular, CD20-positive, B-cell NHL treated in single-arm studies of rituximab administered as a single agent [see Clinical Studies (14.1)]. Most patients received rituximab 375 mg/m^2 weekly for 4 doses.

Table 1 Incidence of Adverse Reactions in ≥5% of Patients with Relapsed or Refractory, Low-Grade or Follicular NHL, Receiving Single-agent Rituximab (N=356) [Adverse reactions observed up to 12 months following rituximab products.] , [Adverse reactions graded for severity by NCI-CTC criteria.]
 | All Grades (%) | Grade 3 and 4 (%)
Any Adverse Reactions | 99 | 57
Body as a Whole | 86 | 10
Fever | 53 | 1
Chills | 33 | 3
Infection | 31 | 4
Asthenia | 26 | 1
Headache | 19 | 1
Abdominal Pain | 14 | 1
Pain | 12 | 1
Back Pain | 10 | 1
Throat Irritation | 9 | 0
Flushing | 5 | 0
Heme and Lymphatic System | 67 | 48
Lymphopenia | 48 | 40
Leukopenia | 14 | 4
Neutropenia | 14 | 6
Thrombocytopenia | 12 | 2
Anemia | 8 | 3
Skin and Appendages | 44 | 2
Night Sweats | 15 | 1
Rash | 15 | 1
Pruritus | 14 | 1
Urticaria | 8 | 1
Respiratory System | 38 | 4
Increased Cough | 13 | 1
Rhinitis | 12 | 1
Bronchospasm | 8 | 1
Dyspnea | 7 | 1
Sinusitis | 6 | 0
Metabolic and Nutritional Disorders | 38 | 3
Angioedema | 11 | 1
Hyperglycemia | 9 | 1
Peripheral Edema | 8 | 0
LDH Increase | 7 | 0
Digestive System | 37 | 2
Nausea | 23 | 1
Diarrhea | 10 | 1
Vomiting | 10 | 1
Nervous System | 32 | 1
Dizziness | 10 | 1
Anxiety | 5 | 1
Musculoskeletal System | 26 | 3
Myalgia | 10 | 1
Arthralgia | 10 | 1
Cardiovascular System | 25 | 3
Hypotension | 10 | 1
Hypertension | 6 | 1

In these single-arm rituximab studies, bronchiolitis obliterans occurred during and up to 6 months after rituximab infusion.

Previously Untreated, Low-Grade or Follicular, NHL

In NHL Study 4, patients in the R-CVP arm experienced a higher incidence of infusional toxicity and neutropenia compared to patients in the CVP arm. The following adverse reactions occurred more frequently (≥5%) in patients receiving R-CVP compared to CVP alone: rash (17% vs. 5%), cough (15% vs. 6%), flushing (14% vs. 3%), rigors (10% vs. 2%), pruritus (10% vs. 1%), neutropenia (8% vs. 3%), and chest tightness (7% vs. 1%) [see Clinical Studies (14.2)].

In NHL Study 5, detailed safety data collection was limited to serious adverse reactions, Grade ≥ 2 infections, and Grade ≥ 3 adverse reactions. In patients receiving rituximab as single-agent maintenance therapy following rituximab plus chemotherapy, infections were reported more frequently compared to the observation arm (37% vs. 22%). Grade 3-4 adverse reactions occurring at a higher incidence (≥ 2%) in the rituximab group were infections (4% vs. 1%) and neutropenia (4% vs. <1%).

In NHL Study 6, the following adverse reactions were reported more frequently (≥5%) in patients receiving rituximab following CVP compared to patients who received no further therapy: fatigue (39% vs. 14%), anemia (35% vs. 20%), peripheral sensory neuropathy (30% vs. 18%), infections (19% vs. 9%), pulmonary toxicity (18% vs. 10%), hepato-biliary toxicity (17% vs. 7%), rash and/or pruritus (17% vs. 5%), arthralgia (12% vs. 3%), and weight gain (11% vs. 4%). Neutropenia was the only Grade 3 or 4 adverse reaction that occurred more frequently (≥2%) in the rituximab arm compared with those who received no further therapy (4% vs. 1%) [see Clinical Studies (14.3)].

DLBCL

In NHL Studies 7 (NCT00003150) and 8, [see Clinical Studies (14.3)], the following adverse reactions, regardless of severity, were reported more frequently (≥5%) in patients age ≥60 years receiving R-CHOP as compared to CHOP alone: pyrexia (56% vs. 46%), lung disorder (31% vs. 24%), cardiac disorder (29% vs. 21%), and chills (13% vs. 4%). Detailed safety data collection in these studies was primarily limited to Grade 3 and 4 adverse reactions and serious adverse reactions.

In NHL Study 8, a review of cardiac toxicity determined that supraventricular arrhythmias or tachycardia accounted for most of the difference in cardiac disorders (4.5% for R-CHOP vs. 1.0% for CHOP).

The following Grade 3 or 4 adverse reactions occurred more frequently among patients in the R-CHOP arm compared with those in the CHOP arm: thrombocytopenia (9% vs. 7%) and lung disorder (6% vs. 3%). Other Grade 3 or 4 adverse reactions occurring more frequently among patients receiving R-CHOP were viral infection (NHL Study 8), neutropenia (NHL Studies 8 and 9 (NCT00064116)), and anemia (NHL Study 9).

CLL

The data below reflect exposure to rituximab in combination with fludarabine and cyclophosphamide in 676 patients with CLL in CLL Study 1 (NCT00281918) or CLL Study 2 (NCT00090051) [) or CLL Study 2 (NCT00090051) [see Clinical Studies (14.5)]. The age range was 30-83 years and 71% were men. Detailed safety data collection in CLL Study 1 was limited to Grade 3 and 4 adverse reactions and serious adverse reactions.

Infusion-related adverse reactions were defined by any of the following adverse events occurring during or within 24 hours of the start of infusion: nausea, pyrexia, chills, hypotension, vomiting, and dyspnea.

In CLL Study 1, the following Grade 3 and 4 adverse reactions occurred more frequently in R-FC-treated patients compared to FC-treated patients: infusion-related reactions (9% in R-FC arm), neutropenia (30% vs. 19%), febrile neutropenia (9% vs. 6%), leukopenia (23% vs. 12%), and pancytopenia (3% vs. 1%).

In CLL Study 2, the following Grade 3 or 4 adverse reactions occurred more frequently in R-FC-treated patients compared to FC-treated patients: infusion-related reactions (7% in R-FC arm), neutropenia (49% vs. 44%), febrile neutropenia (15% vs. 12%), thrombocytopenia (11% vs. 9%), hypotension (2% vs. 0%), and hepatitis B (2% vs. <1%). Fifty-nine percent of R-FC-treated patients experienced an infusion-related reaction of any severity.

6.2 Clinical Trials Experience in Rheumatoid Arthritis

Because clinical trials are conducted under widely varying conditions, adverse reaction rates observed in clinical trials of a drug cannot be directly compared to rates in the clinical trials of another drug and may not reflect the rates observed in practice.

The data presented below reflect the experience in 2578 RA patients treated with rituximab in controlled and long-term studies [Pooled studies: NCT00074438, NCT00422383, NCT00468546, NCT00299130, NCT00282308, NCT00266227, NCT02693210, NCT02093026 and NCT02097745] with a total exposure of 5014 patient-years.

Among all exposed patients, adverse reactions reported in greater than 10% of patients include infusion-related reactions, upper respiratory tract infection, nasopharyngitis, urinary tract infection, and bronchitis.

In placebo-controlled studies, patients received 2 x 500 mg or 2 x 1000 mg intravenous infusions of rituximab or placebo, in combination with methotrexate, during a 24-week period. From these studies, 938 patients treated with rituximab (2 x 1000 mg) or placebo have been pooled (see Table 2). Adverse reactions reported in ≥5% of patients were hypertension, nausea, upper respiratory tract infection, arthralgia, pyrexia and pruritus (see Table 2). The rates and types of adverse reactions in patients who received rituximab 2 x 500 mg were similar to those observed in patients who received rituximab 2 x 1000 mg.

Table 2 [These data are based on 938 patients treated in Phase 2 and 3 studies of rituximab (2 x 1000 mg) or placebo administered in combination with methotrexate.] Incidence of All Adverse Reactions [Coded using MedDRA.] Occurring in ≥2% and at Least 1% Greater than Placebo Among Rheumatoid Arthritis Patients in Clinical Studies Up to Week 24 (Pooled)
Adverse Reactions | Placebo + MTX N=398 n (%) | Rituximab + MTX N=540 n (%)
Hypertension | 21 (5) | 43 (8)
Nausea | 19 (5) | 41 (8)
Upper Respiratory Tract Infection | 23 (6) | 37 (7)
Arthralgia | 14 (4) | 31 (6)
Pyrexia | 8 (2) | 27 (5)
Pruritus | 5 (1) | 26 (5)
Chills | 9 (2) | 16 (3)
Dyspepsia | 3 (< 1) | 16 (3)
Rhinitis | 6 (2) | 14 (3)
Paresthesia | 3 (< 1) | 12 (2)
Urticaria | 3 (< 1) | 12 (2)
Abdominal Pain Upper | 4 (1) | 11 (2)
Throat Irritation | 0 (0) | 11 (2)
Anxiety | 5 (1) | 9 (2)
Migraine | 2 (< 1) | 9 (2)
Asthenia | 1 (< 1) | 9 (2)

Infusion-Related Reactions
In the rituximab RA pooled placebo-controlled studies, 32% of rituximab-treated patients experienced an adverse reaction during or within 24 hours following their first infusion, compared to 23% of placebo-treated patients receiving their first infusion. The incidence of adverse reactions during the 24-hour period following the second infusion, rituximab or placebo, decreased to 11% and 13%, respectively. Acute infusion-related reactions (manifested by fever, chills, rigors, pruritus, urticaria/rash, angioedema, sneezing, throat irritation, cough, and/or bronchospasm, with or without associated hypotension or hypertension) were experienced by 27% of rituximab-treated patients following their first infusion, compared to 19% of placebo-treated patients receiving their first placebo infusion. The incidence of these acute infusion-related reactions following the second infusion of rituximab or placebo decreased to 9% and 11%, respectively. Serious acute infusion-related reactions were experienced by <1% of patients in either treatment group. Acute infusion-related reactions required dose modification (stopping, slowing, or interruption of the infusion) in 10% and 2% of patients receiving rituximab or placebo, respectively, after the first course. The proportion of patients experiencing acute infusion-related reactions decreased with subsequent courses of rituximab. The administration of intravenous glucocorticoids prior to rituximab infusions reduced the incidence and severity of such reactions, however, there was no clear benefit from the administration of oral glucocorticoids for the prevention of acute infusion-related reactions. Patients in clinical studies also received antihistamines and acetaminophen prior to rituximab infusions.

Infections

In the pooled, placebo-controlled studies, 39% of patients in the rituximab group experienced an infection of any type compared to 34% of patients in the placebo group. The most common infections were nasopharyngitis, upper respiratory tract infections, urinary tract infections, bronchitis, and sinusitis.
The incidence of serious infections was 2% in the rituximab-treated patients and 1% in the placebo group.
In the experience with rituximab in 2578 RA patients, the rate of serious infections was 4.31 per 100 patient years. The most common serious infections (≥0.5%) were pneumonia or lower respiratory tract infections, cellulitis and urinary tract infections. Fatal serious infections included pneumonia, sepsis and colitis. Rates of serious infection remained stable in patients receiving subsequent courses. In 185 rituximab-treated RA patients with active disease, subsequent treatment with a biologic DMARD, the majority of which were TNF antagonists, did not appear to increase the rate of serious infection. Thirteen serious infections were observed in 186.1 patient years (6.99 per 100 patient years) prior to exposure and 10 were observed in 182.3 patient years (5.49 per 100 patient years) after exposure.

Cardiovascular Adverse Reactions

In the pooled, placebo-controlled studies, the proportion of patients with serious cardiovascular reactions was 1.7% and 1.3% in the rituximab and placebo treatment groups, respectively. Three cardiovascular deaths occurred during the double-blind period of the RA studies including all rituximab regimens (3/769 = 0.4%) as compared to none in the placebo treatment group (0/389).

In the experience with rituximab in 2578 RA patients, the rate of serious cardiac reactions was 1.93 per 100 patient years. The rate of myocardial infarction (MI) was 0.56 per 100 patient years (28 events in 26 patients), which is consistent with MI rates in the general RA population. These rates did not increase over three courses of rituximab.

Since patients with RA are at increased risk for cardiovascular events compared with the general population, patients with RA should be monitored throughout the infusion and TRUXIMA should be discontinued in the event of a serious or life-threatening cardiac event.

Hypophosphatemia and hyperuricemia

In the pooled, placebo-controlled studies, newly-occurring hypophosphatemia (<2.0 mg/dl) was observed in 12% (67/540) of patients on rituximab versus 10% (39/398) of patients on placebo. Hypophosphatemia was more common in patients who received corticosteroids. Newly-occurring hyperuricemia (>10 mg/dl) was observed in 1.5% (8/540) of patients on rituximab versus 0.3% (1/398) of patients on placebo.

In the experience with rituximab in RA patients, newly-occurring hypophosphatemia was observed in 21% (528/2570) of patients and newly-occurring hyperuricemia was observed in 2% (56/2570) of patients. The majority of the observed hypophosphatemia occurred at the time of the infusions and was transient.

Retreatment in Patients with RA

In the experience with rituximab in RA patients, 2578 patients have been exposed to rituximab and have received up to 10 courses of rituximab in RA clinical trials, with 1890, 1043, and 425 patients having received at least two, three, and four courses, respectively. Most of the patients who received additional courses did so 24 weeks or more after the previous course and none were retreated sooner than 16 weeks. The rates and types of adverse reactions reported for subsequent courses of rituximab were similar to rates and types seen for a single course of rituximab.

In RA Study 2, where all patients initially received rituximab, the safety profile of patients who were retreated with rituximab was similar to those who were retreated with placebo [see Clinical Studies (14.6), and Dosage and Administration (2.5)].

6.3 Clinical Trials Experience in Granulomatosis with Polyangiitis (GPA) (Wegener’s Granulomatosis) and Microscopic Polyangiitis (MPA)

Because clinical trials are conducted under widely varying conditions, adverse reaction rates observed in clinical trials of a drug cannot be directly compared to rates in the clinical trials of another drug and may not reflect the rates observed in practice

Induction Treatment of Adult Patients with Active GPA/MPA (GPA/MPA Study 1)

The data presented below from GPA/MPA Study 1 (NCT00104299) reflect the experience in 197 adult patients with active GPA and MPA treated with rituximab or cyclophosphamide in a single controlled study, which was conducted in two phases: a 6 month randomized, double-blind, double-dummy, active-controlled remission induction phase and an additional 12 month remission maintenance phase [see Clinical Studies (14.7)]. In the 6-month remission induction phase, 197 patients with GPA and MPA were randomized to either rituximab 375 mg/m^2 once weekly for 4 weeks plus glucocorticoids, or oral cyclophosphamide 2 mg/kg daily (adjusted for renal function, white blood cell count, and other factors) plus glucocorticoids to induce remission. Once remission was achieved or at the end of the 6 month remission induction period, the cyclophosphamide group received azathioprine to maintain remission. The rituximab group did not receive additional therapy to maintain remission. The primary analysis was at the end of the 6 month remission induction period and the safety results for this period are described below.

Adverse reactions presented below in Table 3 were adverse events which occurred at a rate of greater than or equal to 10% in the rituximab group. This table reflects experience in 99 GPA and MPA patients treated with rituximab, with a total of 47.6 patient-years of observation and 98 GPA and MPA patients treated with cyclophosphamide, with a total of 47.0 patient-years of observation. Infection was the most common category of adverse events reported (47-62%) and is discussed below.

Table 3 Incidence of All Adverse Reactions Occurring in 10% of rituximab-treated Patients with active GPA and MPA in the GPA/MPA Study 1 Up to Month 6 [The study design allowed for crossover or treatment by best medical judgment, and 13 patients in each treatment group received a second therapy during the 6 month study period.]
Adverse Reaction | Rituximab N=99 n (%) | Cyclophosphamide N=98 n (%)
Nausea | 18 (18%) | 20 (20%)
Diarrhea | 17 (17%) | 12 (12%)
Headache | 17 (17%) | 19 (19%)
Muscle spasms | 17 (17%) | 15 (15%)
Anemia | 16 (16%) | 20 (20%)
Peripheral edema | 16 (16%) | 6 (6%)
Insomnia | 14 (14%) | 12 (12%)
Arthralgia | 13 (13%) | 9 (9%)
Cough | 13 (13%) | 11 (11%)
Fatigue | 13 (13%) | 21 (21%)
Increased ALT | 13 (13%) | 15 (15%)
Hypertension | 12 (12%) | 5 (5%)
Epistaxis | 11 (11%) | 6 (6%)
Dyspnea | 10 (10%) | 11 (11%)
Leukopenia | 10 (10%) | 26 (27%)
Rash | 10 (10%) | 17 (17%)

Infusion-Related Reactions

Infusion-related reactions in GPA/MPA Study 1 were defined as any adverse event occurring within 24 hours of an infusion and considered to be infusion-related by investigators. Among the 99 patients treated with rituximab, 12% experienced at least one infusion-related reaction, compared with 11% of the 98 patients in the cyclophosphamide group.

Infusion-related reactions included cytokine release syndrome, flushing, throat irritation, and tremor. In the rituximab group, the proportion of patients experiencing an infusion-related reaction was 12%, 5%, 4%, and 1% following the first, second, third, and fourth infusions, respectively. Patients were pre-medicated with antihistamine and acetaminophen before each rituximab infusion and were on background oral corticosteroids which may have mitigated or masked an infusion-related reaction; however, there is insufficient evidence to determine whether premedication diminishes the frequency or severity of infusion-related reactions.

Infections

In GPA/MPA Study 1, 62% (61/99) of patients in the rituximab group experienced an infection of any type compared to 47% (46/98) patients in the cyclophosphamide group by Month 6. The most common infections in the rituximab group were upper respiratory tract infections, urinary tract infections, and herpes zoster.

The incidence of serious infections was 11% in the rituximab-treated patients and 10% in the cyclophosphamide treated patients, with rates of approximately 25 and 28 per 100 patient-years, respectively. The most common serious infection was pneumonia.

Hypogammaglobulinemia

Hypogammaglobulinemia (IgA, IgG or IgM below the lower limit of normal) has been observed in patients with GPA and MPA treated with rituximab in GPA/MPA Study 1. At 6 months, in the rituximab group, 27%, 58% and 51% of patients with normal immunoglobulin levels at baseline, had low IgA, IgG and IgM levels, respectively compared to 25%, 50% and 46% in the cyclophosphamide group.

Follow up Treatment of Adult Patients with GPA/MPA who have Achieved Disease Control with Induction Treatment (GPA/MPA Study 2)

In GPA/MPA Study 2 (NCT00748644), an open-label, controlled, clinical study [see Clinical Studies (14.7)], evaluating the efficacy and safety of non-U.S.-licensed rituximab versus azathioprine as follow up treatment in adult patients with GPA, MPA or renal-limited ANCA-associated vasculitis who had achieved disease control after induction treatment with cyclophosphamide, a total of 57 GPA and MPA patients in disease remission received follow up treatment with two 500 mg intravenous infusions of non-U.S.-licensed rituximab, separated by two weeks on Day 1 and Day 15, followed by a 500 mg intravenous infusion every 6 months for 18 months.

The safety profile was consistent with the safety profile for rituximab in RA and GPA and MPA.

Infusion-Related Reactions

In GPA/MPA Study 2, 7/57 (12%) patients in the non-U.S.-licensed rituximab arm reported infusion-related reactions. The incidence of IRR symptoms was highest during or after the first infusion (9%) and decreased with subsequent infusions (<4%). One patient had two serious IRRs, two IRRs led to a dose modification, and no IRRs were severe, fatal, or led to withdrawal from the study.

Infections

In GPA/MPA Study 2, 30/57 (53%) patients in the non-U.S.-licensed rituximab arm and 33/58 (57%) in the azathioprine arm reported infections. The incidence of all grade infections was similar between the arms. The incidence of serious infections was similar in both arms (12%). The most commonly reported serious infection in the group was mild or moderate bronchitis.

Long-term, Observational Study with Rituximab in Patients with GPA/MPA (GPA/MPA Study 3)
In a long-term observational safety study (NCT01613599), 97 patients with GPA or MPA received treatment with rituximab (mean of 8 infusions [range 1-28]) for up to 4 years, according to physician standard practice and discretion. Majority of patients received doses ranging from 500 mg to 1000 mg, approximately every 6 months. The safety profile was consistent with the safety profile for rituximab in RA and GPA and MPA.

6.4 Clinical Trials Experience in Pemphigus Vulgaris (PV)

PV Study 1

PV Study 1 (NCT00784589), a randomized, controlled, multicenter open-label study, evaluated the efficacy and safety of non-U.S.-licensed rituximab in combination with short-term prednisone compared to prednisone monotherapy in 90 patients (74 Pemphigus Vulgaris [PV] patients and 16 Pemphigus Foliaceus [PF] patients) [see Clinical Studies (14.8)]. Safety results for the PV patient population during the 24-month treatment period are described below.

The safety profile of the non-U.S.-licensed rituximab in patients with PV was consistent with that observed in patients with rituximab-treated RA and GPA and MPA [see Adverse Reactions (6.1)].

Adverse reactions from PV Study 1 are presented below in Table 4 and were adverse events which occurred at a rate greater than or equal to 5% among PV patients treated with non-U.S.-licensed rituximab and with at least 2% absolute difference in incidence between the group treated with non-U.S.-licensed rituximab and the prednisone monotherapy group up to Month 24. No patients in the group treated with non-U.S.-licensed rituximab withdrew due to adverse reactions. The clinical study did not include sufficient number of patients to allow for direct comparison of adverse reaction rates between treatment groups.

Table 4 Incidence of All Adverse Reactions Occurring in greater than or equal to 5% Among PV Patients Treated with Non-U.S.-licensed rituximab and with at Least 2% Absolute Difference in Incidence Between the Group Treated with Non-U.S.-licensed rituximab with Short-term Prednisone and the Group Treated with Prednisone Monotherapy in PV Study 1 (Up to Month 24)
Adverse Reaction | Non-U.S.-licensed rituximab + short-term prednisone; N=38; n (%) | Prednisone; N=36; n (%)
Infusion-related reactions* | 22 (58%) | N/A
Depression | 7 (18%) | 4 (11%)
Herpes simplex | 5 (13%) | 1 (3%)
Alopecia | 5 (13%) | 0 (0%)
Fatigue | 3 (8%) | 2 (6%)
Abdominal pain upper | 2 (5%) | 1 (3%)
Conjunctivitis | 2 (5%) | 0 (0%)
Dizziness | 2 (5%) | 0 (0%)
Headache | 2 (5%) | 1 (3%)
Herpes zoster | 2 (5%) | 1 (3%)
Irritability | 2 (5%) | 0 (0%)
Musculoskeletal pain | 2 (5%) | 0 (0%)
Pruritus | 2 (5%) | 0 (0%)
Pyrexia | 2 (5%) | 0 (0%)
Skin disorder | 2 (5%) | 0 (0%)
Skin papilloma | 2 (5%) | 0 (0%)
Tachycardia | 2 (5%) | 0 (0%)
Urticaria | 2 (5%) | 0 (0%)
N/A = not applicable
* Infusion-related reactions included symptoms collected on the next scheduled visit after each infusion, and adverse reactions occurring on the day of or one day after the infusion. The most common infusion-related reactions included headaches, chills, high blood pressure, nausea, asthenia, and pain.

Infusion-Related Reactions

Infusion-related reactions were the most commonly reported adverse drug reactions (58%, 22 patients). All infusion-related reactions were mild to moderate (Grade 1 or 2) except one Grade 3 serious infusion-related reaction (arthralgia) associated with the Month 12 maintenance infusion. The proportion of patients experiencing an infusion-related reaction was 29% (11 patients), 40% (15 patients), 13% (5 patients), and 10% (4 patients) following the first, second, third, and fourth infusions, respectively. No patients were withdrawn from treatment due to infusion-related reactions. Symptoms of infusion-related reactions were similar in type and severity to those seen in RA and GPA and MPA patients [see Adverse Reactions (6.1)].

Infections

Fourteen patients (37%) in the group treated with non-U.S.-licensed rituximab experienced treatment-related infections compared to 15 patients (42%) in the prednisone group. The most common infections in the group treated with non-U.S.-licensed rituximab were herpes simplex, herpes zoster, bronchitis, urinary tract infection, fungal infection, and conjunctivitis. Three patients (8%) in the group treated with non-U.S.-licensed rituximab experienced a total of 5 serious infections (Pneumocystis jirovecii pneumonia, infective thrombosis, intervertebral discitis, lung infection, Staphylococcal sepsis) and 1 patient (3%) in the prednisone group experienced 1 serious infection (Pneumocystis jirovecii pneumonia).

PV Study 2

In PV Study 2 (NCT02383589), a randomized, double-blind, double-dummy, active-comparator, multicenter study evaluating the efficacy and safety of rituximab compared to mycophenolate mofetil (MMF) in patients with moderate-to-severe PV requiring oral corticosteroids, 67 PV patients received treatment with rituximab (initial 1,000 mg IV on Study Day 1 and a second 1,000 mg IV on Study Day 15 repeated at Weeks 24 and 26) for up to 52 weeks [see Clinical Studies (14.8)].

In PV Study 2, ADR defined as adverse events occurring in greater than or equal to 5% of patients in the rituximab arms and assessed as related are shown in Table 5.

Table 5 Incidence of All Adverse Reactions Occurring in greater than or equal to 5% of rituximab-treated Pemphigus Vulgaris Patients (N=67) from PV Study 2 (up to Week 52)
Adverse Reactions | Rituximab; (N=67)
Infusion-related reactions* | 15 (22%)*
Upper respiratory tract infection/Nasopharyngitis | 11 (16%)
Headache | 10 (15%)
Asthenia/Fatigue | 9 (13%)
Oral candidiasis | 6 (9%)
Arthralgia | 6 (9%)
Back pain | 6 (9%)
Urinary tract infection | 5 (8%)
Dizziness | 4 (6%)
*The most common infusion-related reaction symptoms/Preferred Terms for PV Study 2 in the rituximab arm were dyspnoea, erythema, hyperhidrosis, flushing/hot flush, hypotension/low blood pressure and rash/rash pruritic

Infusion-Related Reactions

In PV Study 2, IRRs occurred primarily at the first infusion and the frequency of IRRs decreased with subsequent infusions: 17.9%, 4.7%, 3.5% and 3.5% of patients experienced IRRs at the first, second, third, and fourth infusions, respectively. In 11/15 patients who experienced at least one IRR, the IRRs were Grade 1 or 2. In 4/15 patients, Grade greater than or equal to 3 IRRs were reported and led to discontinuation of rituximab treatment; three of the four patients experienced serious [life-threatening] IRRs. Serious IRRs occurred at the first (2 patients) or second (1 patient) infusion and resolved with symptomatic treatment.

Infections

In PV Study 2, 42/67 patients (62.7%) in the rituximab arm experienced infections. The most common infections in the rituximab arm were upper respiratory tract infection, nasopharyngitis, oral candidiasis and urinary tract infection. Six patients (9%) in the rituximab arm experienced serious infections.

Laboratory Abnormalities

In PV Study 2, in the rituximab arm, transient decreases in T-cell lymphocytes and phosphorus level were very commonly observed post-infusion. In some cases, treatment of hypophosphatemia was required.

Hypogammaglobulinemia (IgG or IgM below the lower limit of normal), including prolonged hypogammaglobulinemia (defined as Ig levels below lower limit of normal for at least 4 months) was observed in PV Study 2. Based on levels less than LLN measured at Week 16, Week 24, Week 40, and Week 52, 16.4% (11/67) of patients with normal baseline immunoglobulins had prolonged hypogammaglobulinemia (10 patients – IgM, 1 patient – both IgG and IgM) after treatment with rituximab.

6.5 Immunogenicity

The observed incidence of anti-drug antibodies is highly dependent on the sensitivity and specificity of the assay. Differences in assay methods preclude meaningful comparisons of the incidence of anti-drug antibodies in the studies described below with the incidence of anti-drug antibodies in other studies, including those of rituximab or of other rituximab products.

Using an ELISA assay, anti-rituximab antibody was detected in 4 of 356 (1.1%) patients with low-grade or follicular NHL receiving single-agent rituximab. Three of the four patients had an objective clinical response.

A total of 273/2,578 (11%) patients with RA tested positive for anti-rituximab antibodies at any time after receiving rituximab. Anti-rituximab antibody positivity was not associated with increased rates of infusion-related reactions or other adverse events. Upon further treatment, the proportions of patients with infusion-related reactions were similar between anti-rituximab antibody positive and negative patients, and most reactions were mild to moderate. Four anti-rituximab antibody positive patients had serious infusion-related reactions, and the temporal relationship between anti-rituximab antibody positivity and infusion-related reaction was variable.

A total of 23/99 (23%) rituximab-treated adult patients with GPA and MPA developed antirituximab antibodies by 18 months in GPA/MPA Study 1. The clinical relevance of anti-rituximab antibody formation in rituximab-treated adult patients is unclear.

Using a new ELISA assay, a total of 19/34 (56%) patients with PV, who were treated with non- U.S.-licensed rituximab, tested positive for anti-rituximab antibodies by 18 months in PV Study 1. In PV Study 2, a total of 20/63 (32%) rituximab-treated PV patients tested positive for ADA by week 52 (19 patients had treatment-inducted ADA and 1 patient had treatment-enhanced ADA). The clinical relevance of anti-rituximab antibody formation in rituximab-treated PV patients is unclear.

6.6 Postmarketing Experience

The following adverse reactions have been identified during post-approval use of rituximab. Because these reactions are reported voluntarily from a population of uncertain size, it is not always possible to reliably estimate their frequency or establish a causal relationship to drug exposure.

- Hematologic: prolonged pancytopenia, marrow hypoplasia, Grade 3-4 prolonged or late-onset neutropenia, hyperviscosity syndrome in Waldenstrom’s macroglobulinemia, prolonged hypogammaglobulinemia [see Warnings and Precautions (5.6)].
- Cardiac: fatal cardiac failure.
- Immune/Autoimmune Events: uveitis, optic neuritis, systemic vasculitis, pleuritis, lupus-like syndrome, serum sickness, polyarticular arthritis, and vasculitis with rash.
- Infection: viral infections, including progressive multifocal leukoencephalopathy (PML), increase in fatal infections in HIV-associated lymphoma, and a reported increased incidence of Grade 3 and 4 infections [see Warnings and Precautions (5.6)].
- Neoplasia: disease progression of Kaposi’s sarcoma.
- Skin: severe mucocutaneous reactions, pyoderma gangrenosum (including genital presentation).
- Gastrointestinal: bowel obstruction and perforation.
- Pulmonary: fatal bronchiolitis obliterans and fatal interstitial lung disease.
- Nervous system: Posterior Reversible Encephalopathy Syndrome (PRES) / Reversible Posterior Leukoencephalopathy Syndrome (RPLS).

7 DRUG INTERACTIONS

Formal drug interaction studies have not been performed with rituximab products. In patients with CLL, rituximab did not alter systemic exposure to fludarabine or cyclophosphamide. In clinical trials of patients with RA, concomitant administration of methotrexate or cyclophosphamide did not alter the pharmacokinetics of rituximab.

8 USE IN SPECIFIC POPULATIONS

8.1 Pregnancy

Risk Summary

Based on human data, rituximab products can cause adverse developmental outcomes including B-cell lymphocytopenia in infants exposed to in-utero [see Clinical Considerations]. In animal reproduction studies, intravenous administration of rituximab to pregnant cynomolgus monkeys during the period of organogenesis caused lymphoid B-cell depletion in the newborn offspring at doses resulting in 80% of the exposure (based on AUC) of those achieved following a dose of 2 grams in humans. Advise pregnant women of the risk to a fetus.

Adverse outcomes in pregnancy occur regardless of the health of the mother or the use of medications. The background risk of major birth defects and miscarriage for the indicated populations is unknown. The estimated background risk in the U.S. general population of major birth defects is 2%-4% and of miscarriage is 15%-20% of clinically recognized pregnancies.

Clinical Considerations

Fetal/Neonatal Adverse Reactions

Observe newborns and infants for signs of infection and manage accordingly.

Data

Human data

Postmarketing data indicate that B-cell lymphocytopenia generally lasting less than six months can occur in infants exposed to rituximab in-utero. Rituximab was detected postnatally in the serum of infants exposed in-utero.

Animal Data

An embryo-fetal developmental toxicity study was performed on pregnant cynomolgus monkeys. Pregnant animals received rituximab via the intravenous route during early gestation (organogenesis period; post coitum days 20 through 50). Rituximab was administered as loading doses on post coitum (PC) Days 20, 21 and 22, at 15, 37.5 or 75 mg/kg/day, and then weekly on PC Days 29, 36, 43 and 50, at 20, 50 or 100 mg/kg/week. The 100 mg/kg/week dose resulted in 80% of the exposure (based on AUC) of those achieved following a dose of 2 grams in humans. Rituximab crosses the monkey placenta. Exposed offspring did not exhibit any teratogenic effects but did have decreased lymphoid tissue B cells.

A subsequent pre-and postnatal reproductive toxicity study in cynomolgus monkeys was completed to assess developmental effects including the recovery of B cells and immune function in infants exposed to rituximab in utero. Animals were treated with a loading dose of 0, 15, or 75 mg/kg every day for 3 days, followed by weekly dosing with 0, 20, or 100 mg/kg dose. Subsets of pregnant females were treated from PC Day 20 through postpartum Day 78, PC Day 76 through PC Day 134, and from PC Day 132 through delivery and postpartum Day 28. Regardless of the timing of treatment, decreased B cells and immunosuppression were noted in the offspring of rituximab-treated pregnant animals. The B-cell counts returned to normal levels, and immunologic function was restored within 6 months postpartum.

8.2 Lactation

There are limited data on the presence of rituximab in human milk and the effect on the breastfed child, and there are no data on the effect on milk production. Rituximab is detected in the milk of lactating cynomolgus monkeys, and maternal IgG is present in human breast milk. Rituximab has also been reported to be excreted at low concentrations in human breast milk. Given that the clinical significance of this finding for children is not known, advise women not to breastfeed during treatment with TRUXIMA and for 6 months after the last dose due to the potential of serious adverse reactions in breastfed children.

8.3 Females and Males of Reproductive Potential

Rituximab products can cause fetal harm when administered to a pregnant woman [see Use in Specific Populations (8.1)].

Pregnancy Testing
Verify pregnancy status in females of reproductive potential prior to initiating TRUXIMA.

Contraception

Females

Advise females of reproductive potential to use effective contraception during treatment with TRUXIMA and for 12 months after the last dose.

8.4 Pediatric Use

The safety and effectiveness of TRUXIMA have not been established in pediatric patients with CLL.

Rheumatoid Arthritis and Pemphigus Vulgaris

The safety and effectivness of TRUXIMA have not been established in pediatric patients with PV or RA.

Rituximab was not studied in pediatric patients with polyarticular juvenile idiopathic arthritis (PJIA) due to concerns regarding the potential for prolonged immunosuppression as a result of B-cell depletion in the developing juvenile immune system.

8.5 Geriatric Use

Diffuse Large B-Cell NHL

Among patients with DLBCL evaluated in three randomized, active-controlled trials, 927 patients received rituximab in combination with chemotherapy. Of these, 396 (43%) were age 65 or greater and 123 (13%) were age 75 or greater. No overall differences in effectiveness were observed between these patients and younger patients. Cardiac adverse reactions, mostly supraventricular arrhythmias, occurred more frequently among elderly patients. Serious pulmonary adverse reactions were also more common among the elderly, including pneumonia and pneumonitis.

Low-Grade or Follicular Non-Hodgkin's Lymphoma

Patients with previously untreated follicular NHL evaluated in NHL Study 5 were randomized to rituximab as single-agent maintenance therapy (n=505) or observation (n=513) after achieving a response to rituximab in combination with chemotherapy. Of these, 123 (24%) patients in the rituximab arm were age 65 or older. No overall differences in safety or effectiveness were observed between these patients and younger patients. Other clinical studies of rituximab in low-grade or follicular, CD20-positive, B-cell NHL did not include sufficient numbers of patients aged 65 and over to determine whether they respond differently from younger subjects.

Chronic Lymphocytic Leukemia

Among patients with CLL evaluated in two randomized active-controlled trials, 243 of 676 rituximab-treated patients (36%) were 65 years of age or older; of these, 100 rituximab-treated patients (15%) were 70 years of age or older.

In exploratory analyses defined by age, there was no observed benefit from the addition of rituximab to fludarabine and cyclophosphamide among patients 70 years of age or older in CLL Study 1 or in CLL Study 2; there was also no observed benefit from the addition of rituximab to fludarabine and cyclophosphamide among patients 65 years of age or older in Study 2 [see Clinical Studies (14.5)]. Patients 70 years or older received lower dose intensity of fludarabine and cyclophosphamide compared to younger patients, regardless of the addition of rituximab. In CLL Study 1, the dose intensity of rituximab was similar in older and younger patients, however in CLL Study 2 older patients received a lower dose intensity of rituximab.

The incidence of Grade 3 and 4 adverse reactions was higher among patients receiving R-FC who were 70 years or older compared to younger patients for neutropenia [44% vs. 31% (CLL Study 1); 56% vs. 39% (CLL Study 2)], febrile neutropenia [16% vs. 6% (NHL Study 10 (NCT00719472))], anemia [5% vs. 2% (CLL Study 1); 21% vs. 10% (CLL Study 2)], thrombocytopenia [19% vs. 8% (CLL Study 2)], pancytopenia [7% vs. 2% (CLL Study 1); 7% vs. 2% (CLL Study 2)] and infections [30% vs. 14% (CLL Study 2)].

Rheumatoid Arthritis

Among the 2578 patients in global RA studies completed to date, 12% were 65-75 years old and 2% were 75 years old and older. The incidences of adverse reactions were similar between older and younger patients. The rates of serious adverse reactions, including serious infections, malignancies, and cardiovascular events were higher in older patients.

Granulomatosis with Polyangiitis (GPA) (Wegener’s Granulomatosis) and Microscopic Polyangiitis

Of the 99 rituximab-treated GPA and MPA patients in GPA/MPA Study 1, 36 (36%) were 65 years old and over, while 8 (8%) were 75 years and over. No overall differences in efficacy were observed between patients that were 65 years old and over and younger patients. The overall incidence and rate of all serious adverse events was higher in patients 65 years old and over. The clinical study did not include sufficient numbers of patients aged 65 and over to determine whether they respond differently from younger subjects.

In GPA/MPA Study 2, 30 (26%) of the enrolled patients were at least 65 years old, of which 12 patients were exposed to non-U.S.-licensed rituximab and 18 were exposed to azathioprine. The clinical study did not include sufficient numbers of patients aged 65 and over to determine whether they respond differently from younger subjects.

Pemphigus Vulgaris

Of the 46 patients treated with non-U.S.-licensed rituximab, 15 (33%) patients were 65 years of age and older. The clinical study did not include sufficient numbers of patients aged 65 and older to determine whether they respond differently from younger patients.

11 DESCRIPTION

Rituximab-abbs is a genetically engineered chimeric murine/human monoclonal IgG1 kappa antibody directed against the CD20 antigen. Rituximab-abbs has an approximate molecular weight of 145 kD.

Rituximab-abbs is produced by mammalian cell (Chinese Hamster Ovary) suspension culture in a nutrient medium.

TRUXIMA (rituximab-abbs) injection is a sterile, clear to opalescent, colorless to pale yellow, preservative-free solution for intravenous infusion. TRUXIMA is supplied at a concentration of 10 mg/mL in either 100 mg/10 mL or 500 mg/50 mL single-dose vials. Each mL of solution contains 10 mg rituximab-abbs, polysorbate 80 (0.7 mg), sodium chloride (9 mg), tri-sodium citrate dihydrate (7.35 mg), and Water for Injection, USP. The pH is 6.5.

12 CLINICAL PHARMACOLOGY

12.1 Mechanism of Action

Rituximab-abbs is a monoclonal antibody. Rituximab products target the CD20 antigen expressed on the surface of pre-B and mature B-lymphocytes. Upon binding to CD20, rituximab products mediate B-cell lysis. Possible mechanisms of cell lysis include complement dependent cytotoxicity (CDC) and antibody dependent cell mediated cytotoxicity (ADCC). B cells are believed to play a role in the pathogenesis of rheumatoid arthritis (RA) and associated chronic synovitis. In this setting, B cells may be acting at multiple sites in the autoimmune/inflammatory process, including through production of rheumatoid factor (RF) and other autoantibodies, antigen presentation, T-cell activation, and/or proinflammatory cytokine production.

12.2 Pharmacodynamics

Non-Hodgkin's Lymphoma (NHL)

In NHL patients, administration of rituximab resulted in depletion of circulating and tissue-based B cells. Among 166 patients in NHL Study 1 (NCT000168740), circulating CD19-positive B cells were depleted within the first three weeks with sustained depletion for up to 6 to 9 months post treatment in 83% of patients.

B-cell recovery began at approximately 6 months and median B-cell levels returned to normal by 12 months following completion of treatment.

There were sustained and statistically significant reductions in both IgM and IgG serum levels observed from 5 through 11 months following rituximab administration; 14% of patients had IgM and/or IgG serum levels below the normal range.

Rheumatoid Arthritis

In RA patients, treatment with rituximab induced depletion of peripheral B lymphocytes, with the majority of patients demonstrating near complete depletion (CD19 counts below the lower limit of quantification, 20 cells/ml) within 2 weeks after receiving the first dose of rituximab. The majority of patients showed peripheral B-cell depletion for at least 6 months. A small proportion of patients (~4%) had prolonged peripheral B-cell depletion lasting more than 3 years after a single course of treatment.

Total serum immunoglobulin levels, IgM, IgG, and IgA were reduced at 6 months with the greatest change observed in IgM. At Week 24 of the first course of rituximab treatment, small proportions of patients experienced decreases in IgM (10%), IgG (2.8%), and IgA (0.8%) levels below the lower limit of normal (LLN). In the experience with rituximab in RA patients during repeated rituximab treatment, 23.3%, 5.5%, and 0.5% of patients experienced decreases in IgM, IgG, and IgA concentrations below LLN at any time after receiving rituximab, respectively. The clinical consequences of decreases in immunoglobulin levels in RA patients treated with rituximab are unclear.

Treatment with rituximab in patients with RA was associated with reduction of certain biologic markers of inflammation such as interleukin-6 (IL-6), C-reactive protein (CRP), serum amyloid protein (SAA), S100 A8/S100 A9 heterodimer complex (S100 A8/9), anti-citrullinated peptide (anti-CCP), and RF.

Granulomatosis with Polyangiitis (GPA) (Wegener’s Granulomatosis) and Microscopic Polyangiitis

In GPA and MPA patients in GPA/MPA Study 1, peripheral blood CD19 B-cells depleted to less than 10 cells/μl following the first two infusions of rituximab, and remained at that level in most (84%) patients through Month 6. By Month 12, the majority of patients (81%) showed signs of B-cell return with counts >10 cells/μL. By Month 18, most patients (87%) had counts >10 cells/μL.

In GPA/MPA Study 2 where patients received non-U.S.-licensed rituximab as two 500 mg intravenous infusions separated by two weeks, followed by a 500 mg intravenous infusion at Month 6, 12, and 18, 70% (30 out of 43) of the rituximab-treated patients with CD19+ peripheral B cells evaluated post-baseline had undetectable CD19+ peripheral B cells at Month 24. At Month 24, all 37 patients with evaluable baseline CD19+ peripheral B cells and Month 24 measurements had lower CD19+ B cells relative to baseline.

12.3 Pharmacokinetics

Non-Hodgkin’s Lymphoma (NHL)

Pharmacokinetics were characterized in 203 NHL patients receiving 375 mg/m^2 rituximab weekly by intravenous infusion for 4 doses. Rituximab was detectable in the serum of patients 3 to 6 months after completion of treatment.

The pharmacokinetic profile of rituximab when administered as 6 infusions of 375 mg/m^2 in combination with 6 cycles of CHOP chemotherapy was similar to that seen with rituximab alone.

Based on a population pharmacokinetic analysis of data from 298 NHL patients who received rituximab once weekly or once every three weeks, the estimated median terminal elimination half-life was 22 days (range, 6.1 to 52 days). Patients with higher CD19-positive cell counts or larger measurable tumor lesions at pretreatment had a higher clearance. However, dose adjustment for pretreatment CD19 count or size of tumor lesion is not necessary. Age and gender had no effect on the pharmacokinetics of rituximab.

Pharmacokinetics were characterized in 21 patients with CLL receiving rituximab according to the recommended dose and schedule. The estimated median terminal half-life of rituximab was 32 days (range, 14 to 62 days).

Rheumatoid Arthritis

Following administration of 2 doses of rituximab in patients with RA, the mean (± S.D.; % CV) concentrations after the first infusion (Cmax first) and second infusion (Cmax second) were 157 (± 46; 29%) and 183 (± 55; 30%) mcg/mL, and 318 (± 86; 27%) and 381 (± 98; 26%) mcg/mL for the 2 x 500 mg and 2 x 1000 mg doses, respectively.

Based on a population pharmacokinetic analysis of data from 2005 RA patients who received rituximab, the estimated clearance of rituximab was 0.335 L/day; volume of distribution was 3.1 L and mean terminal elimination half-life was 18.0 days (range, 5.17 to 77.5 days). Age, weight and gender had no effect on the pharmacokinetics of rituximab in RA patients.

Granulomatosis with Polyangiitis (GPA) (Wegener’s Granulomatosis) and Microscopic Polyangiitis

The PK parameters in adult patients with GPA/MPA receiving 375 mg/m^2 intravenous rituximab once weekly for four doses are summarized in Table 6.

Table 6 Population PK in adult patients (GPA/MPA Study 1) with GPA/MPA
Parameter | Statistic | Adult GPA/MPA (GPA/MPA Study 1)
Parameter | Statistic | Adult GPA/MPA (GPA/MPA Study 1) | N | Number of Patients | 97
Terminal Half-life (days) | Median (Range) | 25 (11 to 52)
AUC0-180d (µg/mL*day) | Median (Range) | 10302 (3653 to 21874)
Clearance (L/day) | Median (Range) | 0.279 (0.113 to 0.653)
Volume of Distribution (L) | Median (Range) | 3.12 (2.42 to 3.91)

The population PK analysis in adults with GPA and MPA showed that male patients and patients with higher BSA or positive anti-rituximab antibody levels have higher clearance. However, further dose adjustment based on gender or antidrug antibody status is not necessary.

Pemphigus Vulgaris

The PK parameters in adult PV patients receiving 1,000 mg IV infusion of rituximab at Days 1, 15, 168, and 182 are summarized in Table 7.

Table 7 Population PK in adult PV patients from PV Study 2
Parameter | Infusion Cycle
 | 1st cycle of 1,000 mg; Day 1 and Day 15; N=67 | 2nd cycle of 1,000 mg; Day 168 and Day 182; N=67
Terminal Half-life (days)
Median | 21.1 | 26.2
(Range) | (9.3 to 36.2) | (16.4 to 42.8)
Clearance (L/day)
Median | 0.30 | 0.24
(Range) | (0.16 to 1.51) | (0.13 to 0.45)
Central Volume of Distribution (L)
Median | 3.49 | 3.49
(Range) | (2.48 to 5.22) | (2.48 to 5.22)

Drug Interaction Studies

Formal drug interaction studies have not been performed with rituximab products.

Drug Interaction Studies

Formal drug interaction studies have not been performed with rituximab products.

13 NONCLINICAL TOXICOLOGY

13.1 Carcinogenesis, Mutagenesis, Impairment of Fertility

No long-term animal studies have been performed to establish the carcinogenic or mutagenic potential of rituximab products or to determine potential effects on fertility in males or females.

14 CLINICAL STUDIES

14.1 Relapsed or Refractory, Low-Grade or Follicular, CD20-Positive, B-Cell NHL

The safety and effectiveness of rituximab in relapsed, refractory CD20+ NHL were demonstrated in 3 single-arm studies enrolling 296 patients.

NHL Study 1

A multicenter, open-label, single-arm study was conducted in 166 patients with relapsed or refractory, low-grade or follicular, B-cell NHL who received 375 mg/m^2 of rituximab given as an intravenous infusion weekly for 4 doses. Patients with tumor masses > 10 cm or with > 5000 lymphocytes/µL in the peripheral blood were excluded from the study.

Results are summarized in Table 5. The median time to onset of response was 50 days. Disease-related signs and symptoms (including B-symptoms) resolved in 64% (25/39) of those patients with such symptoms at study entry.

NHL Study 2

In a multicenter, single-arm study, 37 patients with relapsed or refractory, low-grade NHL received 375 mg/m^2 of rituximab weekly for 8 doses. Results are summarized in Table 5.

NHL Study 3

In a multicenter, single-arm study, 60 patients received 375 mg/m^2 of rituximab weekly for 4 doses. All patients had relapsed or refractory, low-grade or follicular, B-cell NHL and had achieved an objective clinical response to rituximab administered 3.8–35.6 months (median 14.5 months) prior to retreatment with rituximab. Of these 60 patients, 5 received more than one additional course of rituximab. Results are summarized in Table 8.

Bulky Disease

In pooled data from studies 1 and 3, 39 patients with bulky (single lesion > 10 cm in diameter) and relapsed or refractory, low-grade NHL received rituximab 375 mg/m^2 weekly for 4 doses. Results are summarized in Table 8.

Table 8 Summary of Rituximab Efficacy Data in NHL by Schedule and Clinical Setting
 | NHL Study 1 Weekly × 4 N=166 | NHL Study 2 Weekly × 8 N=37 | NHL Study 1 and NHL Study 3 Bulky disease, Weekly × 4 N=39 [Six of these patients are included in the first column. Thus, data from 296 intent-to-treat patients are provided in this table.] | NHL Study 3 Retreatment, Weekly × 4 N=60
Overall Response Rate | 48% | 57% | 36% | 38%
Complete Response Rate | 6% | 14% | 3% | 10%
Median Duration of Response | 11.2 | 13.4 | 6.9 | 15.0
(Months) [Range] [Kaplan-Meier projected with observed range.] , [+ indicates an ongoing response.] , [Duration of response: interval from the onset of response to disease progression.] | [1.9 to 42.1+] | [2.5 to 36.5+] | [2.8 to 25.0+] | [3.0 to 25.1+]

14.2 Previously Untreated, Low-Grade or Follicular, CD20-Positive, B-Cell NHL

The safety and effectiveness of rituximab in previously untreated, low-grade or follicular, CD20+ NHL were demonstrated in 3 randomized, controlled trials enrolling 1,662 patients.

NHL Study 4

A total of 322 patients with previously untreated follicular NHL were randomized (1:1) to receive up to eight 3-week cycles of CVP chemotherapy alone (CVP) or in combination with rituximab 375 mg/m2 on Day 1 of each cycle (R-CVP) in an open-label, multicenter study. The main outcome measure of the study was progression-free survival (PFS) defined as the time from randomization to the first of progression, relapse, or death.

Twenty-six percent of the study population was >60 years of age, 99% had Stage III or IV disease, and 50% had an International Prognostic Index (IPI) score 2. The results for PFS as determined by a blinded, independent assessment of progression are presented in Table 9. The point estimates may be influenced by the presence of informative censoring. The PFS results based on investigator assessment of progression were similar to those obtained by the independent review assessment.

Table 9 Efficacy Results in NHL Study 4
 | Study Arm
 | R-CVP N=162 | CVP N=160
Median PFS (years) [p<0.0001, two-sided stratified log-rank test.] | 2.4 | 1.4
Hazard ratio (95% CI) [Estimates of Cox regression stratified by center.] | 0.44 (0.29, 0.65)

NHL Study 5

An open-label, multicenter, randomized (1:1) study was conducted in 1,018 patients with previously untreated follicular NHL who achieved a response (CR or PR) to rituximab in combination with chemotherapy. Patients were randomized to rituximab as single-agent maintenance therapy, 375 mg/m^2 every 8 weeks for up to 12 doses or to observation. Rituximab was initiated at 8 weeks following completion of chemotherapy. The main outcome measure of the study was progression-free survival (PFS), defined as the time from randomization in the maintenance/observation phase to progression, relapse, or death, as determined by independent review.

Of the randomized patients, 40% were 60 years of age, 70% had Stage IV disease, 96% had ECOG performance status (PS) 01, and 42% had FLIPI scores of 35. Prior to randomization to maintenance therapy, patients had received R-CHOP (75%), R-CVP (22%), or R-FCM (3%); 71% had a complete or unconfirmed complete response and 28% had a partial response.

PFS was longer in patients randomized to rituximab as single agent maintenance therapy (HR: 0.54, 95% CI: 0.42, 0.70). The PFS results based on investigator assessment of progression were similar to those obtained by the independent review assessment.

Figure 1 Kaplan-Meier Plot of IRC Assessed PFS in NHL Study 5

NHL Study 6

A total of 322 patients with previously untreated low-grade, B-cell NHL who did not progress after 6 or 8 cycles of CVP chemotherapy were enrolled in an open-label, multicenter, randomized trial. Patients were randomized (1:1) to receive rituximab, 375 mg/m^2 intravenous infusion, once weekly for 4 doses every 6 months for up to 16 doses or no further therapeutic intervention. The main outcome measure of the study was progression-free survival defined as the time from randomization to progression, relapse, or death. Thirty-seven percent of the study population was >60 years of age, 99% had Stage III or IV disease, and 63% had an IPI score ≥2.

There was a reduction in the risk of progression, relapse, or death (hazard ratio estimate in the range of 0.36 to 0.49) for patients randomized to rituximab as compared to those who received no additional treatment.

14.3 Diffuse Large B-Cell NHL (DLBCL)

The safety and effectiveness of rituximab were evaluated in three randomized, active-controlled, open-label, multicenter studies with a collective enrollment of 1854 patients. Patients with previously untreated diffuse large B-cell NHL received rituximab in combination with cyclophosphamide, doxorubicin, vincristine, and prednisone (CHOP) or other anthracycline-based chemotherapy regimens.

NHL Study 7
A total of 632 patients age ≥60 years with DLBCL (including primary mediastinal B-cell lymphoma) were randomized in a 1:1 ratio to treatment with CHOP or R-CHOP. Patients received 6 or 8 cycles of CHOP, each cycle lasting 21 days. All patients in the R-CHOP arm received 4 doses of rituximab 375 mg/m^2 on Days -7 and -3 (prior to Cycle 1) and 48-72 hours prior to Cycles 3 and 5. Patients who received 8 cycles of CHOP also received rituximab prior to Cycle 7. The main outcome measure of the study was progression-free survival, defined as the time from randomization to the first of progression, relapse, or death. Responding patients underwent a second randomization to receive rituximab or no further therapy.

Among all enrolled patients, 62% had centrally confirmed DLBCL histology, 73% had Stage III-IV disease, 56% had IPI scores ≥2, 86% had ECOG performance status of <2, 57% had elevated LDH levels, and 30% had two or more extranodal disease sites involved. Efficacy results are presented in Table 7. These results reflect a statistical approach which allows for an evaluation of rituximab administered in the induction setting that excludes any potential impact of rituximab given after the second randomization.

Analysis of results after the second randomization in NHL Study 7 demonstrates that for patients randomized to R-CHOP, additional rituximab exposure beyond induction was not associated with further improvements in progression-free survival or overall survival.

NHL Study 8

A total of 399 patients with DLBCL, age ≥60 years, were randomized in a 1:1 ratio to receive CHOP or R-CHOP. All patients received up to eight 3-week cycles of CHOP induction; patients in the R-CHOP arm received rituximab 375 mg/m^2 on Day 1 of each cycle. The main outcome measure of the study was event-free survival, defined as the time from randomization to relapse, progression, change in therapy, or death from any cause. Among all enrolled patients, 80% had Stage III or IV disease, 60% of patients had an age-adjusted IPI ≥2, 80% had ECOG performance status scores <2, 66% had elevated LDH levels, and 52% had extranodal involvement in at least two sites. Efficacy results are presented in Table 7.

NHL Study 9

A total of 823 patients with DLBCL, aged 18-60 years, were randomized in a 1:1 ratio to receive an anthracycline-containing chemotherapy regimen alone or in combination with rituximab. The main outcome measure of the study was time to treatment failure, defined as time from randomization to the earliest of progressive disease, failure to achieve a complete response, relapse, or death. Among all enrolled patients, 28% had Stage III-IV disease, 100% had IPI scores of 1, 99% had ECOG performance status of <2, 29% had elevated LDH levels, 49% had bulky disease, and 34% had extranodal involvement. Efficacy results are presented in Table 10.

Table 10 Efficacy Results in NHL Studies 7, 8, and 9
 | NHL Study 7 (n = 632) |  |  | NHL Study 8 (n = 399) |  |  | NHL Study 9 (n = 823)
 | R-CHOP | CHOP |  | R-CHOP | CHOP |  | R-Chemo | Chemo
Main outcome | Progression-free survival (years) |  |  | Event-free survival (years) |  |  | Time to treatment failure (years)
Median of main outcome measure | 3.1 | 1.6 |  | 2.9 | 1.1 |  | NE [NE=Not reliably estimable.] | NE
Hazard ratio [R-CHOP vs. CHOP.] | 0.69 [Significant at p <0.05, 2-sided.] |  |  | 0.60 |  |  | 0.45
Overall survival at 2 years [Kaplan-Meier estimates.] | 74% | 63% |  | 69% | 58% |  | 95% | 86%
Hazard ratio | 0.72 |  |  | 0.68 |  |  | 0.40

In NHL Study 8, overall survival estimates at 5 years were 58% vs. 46% for R-CHOP and CHOP, respectively.

14.4 Ninety-Minute Infusions in Previously Untreated Follicular NHL and DLBCL

In NHL Study 10, a total of 363 patients with previously untreated follicular NHL (n=113) or DLBCL (n=250) were evaluated in a prospective, open-label, multi-center, single-arm trial for the safety of 90-minute rituximab infusions. Patients with follicular NHL received rituximab 375 mg/m^2 plus CVP chemotherapy. Patients with DLBCL received rituximab 375 mg/m^2 plus CHOP chemotherapy. Patients with clinically significant cardiovascular disease were excluded from the study. Patients were eligible for a 90-minute infusion at Cycle 2 if they did not experience a Grade 3-4 infusion-related adverse event with Cycle 1 and had a circulating lymphocyte count ≤ 5000/mm^3 before Cycle 2. All patients were pre-medicated with acetaminophen and an antihistamine and received the glucocorticoid component of their chemotherapy prior to rituximab infusion. The main outcome measure was the development of Grade 3-4 infusion-related reactions on the day of, or day after, the 90-minute infusion at Cycle 2 [see Adverse Reactions (6.1)].

Eligible patients received their Cycle 2 rituximab infusion over 90 minutes as follows: 20% of the total dose given in the first 30 minutes and the remaining 80% of the total dose given over the next 60 minutes [see Dosage and Administration (2.1)]. Patients who tolerated the 90-minute rituximab infusion at Cycle 2 continued to receive subsequent rituximab infusions at the 90-minute infusion rate for the remainder of the treatment regimen (through Cycle 6 or Cycle 8).

The incidence of Grade 3-4 infusion-related reactions at Cycle 2 was 1.1% (95% CI [0.3%, 2.8%]) among all patients, 3.5% (95% CI [1.0%, 8.8%]) for those patients treated with R-CVP, and 0.0% (95% CI [0.0%, 1.5%]) for those patients treated with R-CHOP. For Cycles 2-8, the incidence of Grade 3-4 infusion-related reactions was 2.8% (95% CI [1.3%, 5.0%]). No acute fatal infusion-related reactions were observed.

14.5 Chronic Lymphocytic Leukemia (CLL)

The safety and effectiveness of rituximab were evaluated in two randomized (1:1) multicenter open-label studies comparing FC alone or in combination with rituximab for up to 6 cycles in patients with previously untreated CLL [CLL Study 1 (n=817)] or previously treated CLL [CLL Study 2 (n=552)]. Patients received fludarabine 25 mg/m^2/day and cyclophosphamide 250 mg/m^2/day on days 1, 2 and 3 of each cycle, with or without rituximab. In both studies, seventy-one percent of CLL patients received 6 cycles and 90% received at least 3 cycles of rituximab-based therapy.

In CLL Study11, 30% of patients were 65 years or older, 31% were Binet stage C, 45% had B symptoms, more than 99% had ECOG performance status (PS) 0-1, 74% were male, and 100% were White. In CLL Study 2, 44% of patients were 65 years or older, 28% had B symptoms, 82% received a prior alkylating drug, 18% received prior fludarabine, 100% had ECOG PS 0-1, 67% were male and 98% were White.

The main outcome measure in both studies was progression-free survival (PFS), defined as the time from randomization to progression, relapse, or death, as determined by investigators (CLL Study 1) or an independent review committee (CLL Study 2). The investigator assessed results in CLL Study 2 were supportive of those obtained by the independent review committee. Efficacy results are presented in Table 11.

Table 11 Efficacy Results in CLL Studies 1 and 2
 | CLL Study 1 [As defined in 1996 National Cancer Institute Working Group guidelines.] (Previously untreated) |  | CLL Study 2 (Previously treated)
 | R-FC N = 408 | FC N = 409 | R-FC N = 276 | FC N = 276
Median PFS (months) | 39.8 | 31.5 | 26.7 | 21.7
Hazard ratio (95% CI) | 0.56 (0.43, 0.71) |  | 0.76 (0.6, 0.96)
P value (Log-Rank test) | < 0.01 |  | 0.02
Response rate (95% CI) | 86% (82, 89) | 73% (68, 77) | 54% (48, 60) | 45% (37, 51)

Across both studies, 243 of 676 rituximab-treated patients (36%) were 65 years of age or older and 100 rituximab-treated patients (15%) were 70 years of age or older. The results of exploratory subset analyses in elderly patients are presented in Table 12.

Table 12 Efficacy Results in CLL Studies 1 and 2 in Subgroups Defined by Age [From exploratory analyses.]
 | CLL Study 1 |  | CLL Study 2
Age subgroup | Number of Patients | Hazard Ratio for PFS (95% CI) | Number of Patients | Hazard Ratio for PFS (95% CI)
Age < 65 yrs | 572 | 0.52 (0.39, 0.70) | 313 | 0.61 (0.45, 0.84)
Age ≥ 65 yrs | 245 | 0.62 (0.39, 0.99) | 233 | 0.99 (0.70, 1.40)
Age < 70 yrs | 736 | 0.51 (0.39, 0.67) | 438 | 0.67 (0.51, 0.87)
Age ≥ 70 yrs | 81 | 1.17 (0.51, 2.66) | 108 | 1.22 (0.73, 2.04)

14.6 Rheumatoid Arthritis (RA)

Reducing the Signs and Symptoms: Initial and Re-Treatment Courses

The efficacy and safety of rituximab were evaluated in two randomized, double-blind, placebo-controlled studies of adult patients with moderately to severely active RA who had a prior inadequate response to at least one TNF inhibitor. Patients were 18 years of age or older, diagnosed with active RA according to American College of Rheumatology (ACR) criteria, and had at least 8 swollen and 8 tender joints.

In RA Study 1 (NCT00468546), patients were randomized to receive either rituximab 2 x 1000 mg + MTX or placebo + MTX for 24 weeks. Further courses of rituximab 2 x 1000 mg + MTX were administered in an open label extension study at a frequency determined by clinical evaluation, but no sooner than 16 weeks after the preceding course of rituximab. In addition to the intravenous premedication, glucocorticoids were administered orally on a tapering schedule from baseline through Day 14. The proportions of patients achieving ACR 20, 50, and 70 responses at Week 24 of the placebo-controlled period are shown in Table 13.

In RA Study 2 (NCT00266227), all patients received the first course of rituximab 2 x 1000 mg + MTX. Patients who experienced ongoing disease activity were randomized to receive a second course of either rituximab 2 x 1000 mg + MTX or placebo + MTX, the majority between Weeks 2428. The proportions of patients achieving ACR 20, 50, and 70 responses at Week 24, before the re-treatment course, and at Week 48, after retreatment, are shown in Table 13.

Table 13 ACR Responses in RA Study 1 and RA Study 2 (Percent of Patients) (Modified Intent-to-Treat Population)
Inadequate Response to TNF Antagonists
RA Study 1 24 Week Placebo-Controlled (Week 24) |  |  |  |  | RA Study 2 Placebo-Controlled Retreatment (Week 24 and Week 48)
Response | Placebo + MTX n = 201 | Rituximab+ MTX n = 298 | Treatment Difference (Rituximab Placebo) [For RA Study 1, weighted difference stratified by region (US, rest of the world) and Rheumatoid Factor (RF) status (positive > 20 IU/mL, negative < 20 IU/mL) at baseline; For RA Study 2, weighted difference stratified by RF status at baseline and 20% improvement from baseline in both SJC and TJC at Week 24 (Yes/No).] (95% CI) |  | Response | Placebo + MTX Retreatment n = 157 | Rituximab+ MTX Retreatment n = 318 | Treatment Difference (Rituximab Placebo) [In RA Study 2, all patients received a first course of rituximab 2 x 1000 mg. Patients who experienced ongoing disease activity were randomized to receive a second course of either rituximab 2 x 1000 mg + MTX or placebo + MTX at or after Week 24.] , [Since all patients received a first course of rituximab, no comparison between Placebo + MTX and rituximab + MTX is made at Week 24.] ,(95% CI)
ACR20 |  |  |  |  | ACR20
Week 24 | 18% | 51% | 33% (26%, 41%) |  | Week 24 | 48% | 45% | NA
 |  |  |  |  | Week 48 | 45% | 54% | 11% (2%, 20%)
ACR50 |  |  |  |  | ACR50
Week 24 | 5% | 27% | 21% (15%, 27%) |  | Week 24 | 27% | 21% | NA
 |  |  |  |  | Week 48 | 26% | 29% | 4% (-4%, 13%)
ACR70 |  |  |  |  | ACR70
Week 24 | 1% | 12% | 11% (7%, 15%) |  | Week 24 | 11% | 8% | NA
 |  |  |  |  | Week 48 | 13% | 14% | 1% (-5%, 8%)

Improvement was also noted for all components of ACR response following treatment with rituximab, as shown in Table 14.

Table 14 Components of ACR Response at Week 24 in RA Study 1 (Modified Intent-to-Treat Population)
Inadequate Response to TNF Antagonists
Parameter (median) | Placebo + MTX (n = 201) |  | Rituximab+ MTX (n = 298)
Parameter (median) | Baseline | Wk 24 | Baseline | Wk 24
Tender Joint Count | 31.0 | 27.0 | 33.0 | 13.0
Swollen Joint Count | 20.0 | 19.0 | 21.0 | 9.5
Physician Global Assessment [Visual Analogue Scale: 0 = best, 100 = worst.] | 71.0 | 69.0 | 71.0 | 36.0
Patient Global Assessment | 73.0 | 68.0 | 71.0 | 41.0
Pain | 68.0 | 68.0 | 67.0 | 38.5
Disability Index (HAQ) [Disability Index of the Health Assessment Questionnaire: 0 = best, 3 = worst.] | 2.0 | 1.9 | 1.9 | 1.5
CRP (mg/dL) | 2.4 | 2.5 | 2.6 | 0.9

The time course of ACR 20 response for RA Study 1 is shown in Figure 2. Although both treatment groups received a brief course of intravenous and oral glucocorticoids, resulting in similar benefits at Week 4, higher ACR 20 responses were observed for the rituximab group by Week 8. A similar proportion of patients achieved these responses through Week 24 after a single course of treatment (2 infusions) with rituximab. Similar patterns were demonstrated for ACR 50 and 70 responses.

Figure 2 Percent of Patients Achieving ACR 20 Response by Visit [The same patients may not have responded at each time point.] RA Study 1 (Inadequate Response to TNF Antagonists)

Radiographic Response

In RA Study 1, structural joint damage was assessed radiographically and expressed as changes in Genant-modified Total Sharp Score (TSS) and its components, the erosion score (ES) and the joint space narrowing (JSN) score. Rituximab + MTX slowed the progression of structural damage compared to placebo + MTX after 1 year as shown in Table 15.

Table 15 Mean Radiographic Change From Baseline to 104 Weeks in RA Study 1
Inadequate Response to TNF Antagonists
Parameter | Rituximab 2 × 1000 mg + MTX [Patients received up to 2 years of treatment with rituximab + MTX.] | Placebo + MTX [Patients receiving Placebo + MTX. Patients receiving Placebo + MTX could have received retreatment with rituximab + MTX from Week 16 onward.] | Treatment Difference (Placebo Rituximab) | 95% CI
Change during First Year
TSS | 0.66 | 1.77 | 1.11 | (0.47, 1.75)
ES | 0.44 | 1.19 | 0.75 | (0.32, 1.19)
JSN Score | 0.22 | 0.58 | 0.36 | (0.10, 0.62)
Change during Second Year [Based on radiographic scoring following 104 weeks of observation.]
TSS | 0.48 | 1.04
ES | 0.28 | 0.62
JSN Score | 0.20 | 0.42

In RA Study 1 and its open-label extension, 70% of patients initially randomized to rituximab + MTX and 72% of patients initially randomized to placebo + MTX were evaluated radiographically at Year 2. As shown in Table 15, progression of structural damage in rituximab + MTX patients was further reduced in the second year of treatment.

Following 2 years of treatment with rituximab + MTX, 57% of patients had no progression of structural damage. During the first year, 60% of rituximab + MTX treated patients had no progression, defined as a change in TSS of zero or less compared to baseline, compared to 46% of placebo + MTX treated patients. In their second year of treatment with rituximab + MTX, more patients had no progression than in the first year (68% vs. 60%), and 87% of the rituximab + MTX treated patients who had no progression in the first year also had no progression in the second year.

Lesser Efficacy of 500 Vs. 1000 mg Treatment Courses for Radiographic Outcomes

RA Study 3 (NCT00299104) is a randomized, double-blind, placebo-controlled study which evaluated the effect of placebo + MTX compared to rituximab 2 x 500 mg + MTX and rituximab 2 x 1000 mg + MTX treatment courses in MTX-naïve RA patients with moderately to severely active disease. Patients received a first course of two infusions of rituximab or placebo on Days 1 and 15. MTX was initiated at 7.5 mg/week and escalated up to 20 mg/week by Week 8 in all three treatment arms. After a minimum of 24 weeks, patients with ongoing disease activity were eligible to receive re-treatment with additional courses of their assigned treatment. After one year of treatment, the proportion of patients achieving ACR 20/50/70 responses were similar in both rituximab dose groups and were higher than in the placebo group. However, with respect to radiographic scores, only the rituximab 1000 mg treatment group demonstrated a statistically significant reduction in TSS: a change of 0.36 units compared to 1.08 units for the placebo group, a 67% reduction.

Physical Function Response

RA Study 4 (NCT00299130) is a randomized, double-blind, placebo-controlled study in adult RA patients with moderately to severely active disease with inadequate response to MTX. Patients were randomized to receive an initial course of rituximab 500 mg, rituximab 1000 mg, or placebo in addition to background MTX.

Physical function was assessed at Weeks 24 and 48 using the Health Assessment Questionnaire Disability Index (HAQ-DI). From baseline to Week 24, a greater proportion of rituximab-treated patients had an improvement in HAQ-DI of at least 0.22 (a minimal clinically important difference) and a greater mean HAQ-DI improvement compared to placebo, as shown in Table 16. HAQ-DI results for the rituximab 500 mg treatment group were similar to the rituximab 1000 mg treatment group; however radiographic responses were not assessed (see Dosing Precaution in the Radiographic Responses section above). These improvements were maintained at 48 weeks.

Table 16 Improvement from Baseline in Health Assessment Questionnaire Disability Index (HAQ-DI) at Week 24 in RA Study 4
 | Placebo + MTX n = 172 | Rituximab 2 × 1000 mg + MTX n = 170 | Treatment Difference (Rituximab Placebo) [Adjusted difference stratified by region (US, rest of the world) and rheumatoid factor (RF) status (positive 20 IU/mL, negative < 20 IU/mL) at baseline.] (95% CI)
Mean Improvement from Baseline | 0.19 | 0.42 | 0.23 (0.11, 0.34)
Percent of patients with "Improved" score (Change from Baseline MCID) [Minimal Clinically Important Difference: MCID for HAQ = 0.22.] | 48% | 58% | 11% (0%, 21%)

14.7 Granulomatosis with Polyangiitis (GPA) (Wegener’s Granulomatosis) and Microscopic Polyangiitis (MPA)

Induction Treatment of Adult Patients with Active Disease (GPA/MPA Study 1)

A total of 197 adult patients with active, severe GPA and MPA (two forms of ANCA Associated Vasculitides) were treated in a randomized, double-blind, active-controlled, multicenter, non-inferiority study, conducted in two phases a 6 month remission induction phase and a 12 month remission maintenance phase. Patients were 15 years of age or older, diagnosed with GPA (75% of patients) or MPA (24% of patients) according to the Chapel Hill Consensus conference criteria (1% of the patients had unknown vasculitis type). All patients had active disease, with a Birmingham Vasculitis Activity Score for Granulomatosis with Polyangiitis (BVAS/GPA) 3, and their disease was severe, with at least one major item on the BVAS/GPA. Ninety-six (49%) of patients had new disease and 101 (51%) of patients had relapsing disease.

Patients in both arms received 1000 mg of pulse intravenous methylprednisolone per day for 1 to 3 days within 14 days prior to initial infusion. Patients were randomized in a 1:1 ratio to receive either rituximab 375 mg/m^2 once weekly for 4 weeks or oral cyclophosphamide 2 mg/kg daily for 3 to 6 months in the remission induction phase. Patients were pre-medicated with antihistamine and acetaminophen prior to rituximab infusion. Following intravenous corticosteroid administration, all patients received oral prednisone (1 mg/kg/day, not exceeding 80 mg/day) with pre-specified tapering. Once remission was achieved or at the end of the 6 month remission induction period, the cyclophosphamide group received azathioprine to maintain remission. The rituximab group did not receive additional therapy to maintain remission. The main outcome measure for both GPA and MPA patients was achievement of complete remission at 6 months defined as a BVAS/GPA of 0, and off glucocorticoid therapy. The pre-specified non-inferiority margin was a treatment difference of 20%. As shown in Table 17, the study demonstrated non-inferiority of rituximab to cyclophosphamide for complete remission at 6 months.

Table 17 Percentage of Patients with GPA/MPA Who Achieved Complete Remission at 6 Months (Intent-to-Treat Population)
 | Rituximab (n = 99) | Cyclophosphamide (n = 98) | Treatment Difference (Rituximab Cyclophosphamide)
Rate | 64% | 53% | 11%
95.1% [The 95.1% confidence level reflects an additional 0.001 alpha to account for an interim efficacy analysis.] CI | (54%, 73%) | (43%, 63%) | (-3%, 24%) [non-inferiority was demonstrated because the lower bound was higher than the prespecified non-inferiority margin (-3% > -20%).]

Complete Remission (CR) at 12 and 18 months

In the rituximab group, 44% of patients achieved CR at 6 and 12 months, and 38% of patients achieved CR at 6, 12, and 18 months. In patients treated with cyclophosphamide (followed by azathioprine for maintenance of CR), 38% of patients achieved CR at 6 and 12 months, and 31% of patients achieved CR at 6, 12, and 18 months.

Retreatment of Flares with Rituximab

Based upon investigator judgment, 15 patients received a second course of rituximab therapy for treatment of relapse of disease activity which occurred between 8 and 17 months after the induction treatment course of rituximab.

Follow up Treatment of Adult Patients with GPA/MPA who have achieved disease control with other Immunosuppressant (GPA/MPA Study 2)

A total of 115 patients (86 with GPA, 24 with MPA, and 5 with renal-limited ANCA-associated vasculitis) in disease remission were randomized to receive azathioprine (58 patients) or non-U.S.-licensed rituximab (57 patients) in this open-label, prospective, multi-center, randomized, active-controlled study. Eligible patients were 21 years and older and had either newly diagnosed (80%) or relapsing disease (20%). A majority of the patients were ANCA-positive. Remission of active disease was achieved using a combination of glucocorticoids and cyclophosphamide. Within a maximum of 1 month after the last cyclophosphamide dose, eligible patients (based on BVAS of 0), were randomized in a 1:1 ratio to receive either non-U.S.-licensed rituximab or azathioprine.

The non-U.S.-licensed rituximab was administered as two 500 mg intravenous infusions separated by two weeks (on Day 1 and Day 15) followed by a 500 mg intravenous infusion every 6 months for 18 months. Azathioprine was administered orally at a dose of 2 mg/kg/day for 12 months, then 1.5 mg/kg/day for 6 months, and finally 1 mg/kg/day for 4 months; treatment was discontinued after 22 months. Prednisone treatment was tapered and then kept at a low dose (approximately 5 mg per day) for at least 18 months after randomization. Prednisone dose tapering and the decision to stop prednisone treatment after month 18 were left at the investigators discretion.

Planned follow-up was until month 28 (10 or 6 months, respectively, after the last non-U.S.-licensed rituximab infusion or azathioprine dose). The primary endpoint was the occurrence of major relapse (defined by the reappearance of clinical and/or laboratory signs of vasculitis activity that could lead to organ failure or damage, or could be life threatening) through month 28.

By month 28, major relapse occurred in 3 patients (5%) in the non-U.S.-licensed rituximab group and 17 patients (29%) in the azathioprine group.

The observed cumulative incidence rate of first major relapse during the 28 months was lower in patients on non-U.S.-licensed rituximab relative to azathioprine (Figure 3).

Figure 3 Cumulative Incidence Over Time of First Major Relapse in Patients with GPA/MPA

Patients were censored at the last follow-up dates if they had no event

14.8 Pemphigus Vulgaris (PV)

PV Study 1 (NCT00784589)

Non-U.S.-licensed rituximab in combination with short-term prednisone was compared to prednisone monotherapy as first-line treatment in 90 newly diagnosed adult patients with moderate to severe pemphigus (74 Pemphigus Vulgaris [PV] and 16 Pemphigus Foliaceus [PF]) in this randomized, open-label, controlled, multicenter study (PV Study 1). Patients were between 19 and 79 years of age and had not received prior therapies for pemphigus. In the PV population, 5 (13%) patients in the group treated with non-U.S.-licensed rituximab and 3 (8%) patients in the prednisone group had moderate disease and 33 (87%) patients in the group treated with non-U.S.-licensed rituximab and 33 (92%) patients in the prednisone group had severe disease according to disease severity defined by Harman’s criteria.

Patients were stratified by baseline disease severity (moderate or severe) and randomized 1:1 to receive either the non-U.S.-licensed rituximab and short-term prednisone or long-term prednisone monotherapy. Patients were pre-medicated with antihistamine, acetaminophen and methylprednisolone prior to infusion of the non-U.S.-licensed rituximab. Patients randomized to the group treated with non-U.S.-licensed rituximab received an initial intravenous infusion of 1,000 mg non-U.S.-licensed rituximab on Study Day 1 in combination with a short-term regimen of 0.5 mg/kg/day oral prednisone tapered off over 3 months if they had moderate disease or 1 mg/kg/day oral prednisone tapered off over 6 months if they had severe disease. All patients received a second intravenous infusion of 1,000 mg non-U.S.-licensed rituximab on Study Day 15. Maintenance infusions of 500 mg non-U.S.-licensed rituximab were administered at Months 12 and 18. Patients randomized to the prednisone monotherapy group received an initial 1 mg/kg/day oral prednisone tapered off over 12 months if they had moderate disease or 1.5 mg/kg/day oral prednisone tapered off over 18 months if they had severe disease. Patients in the group treated with non-U.S.-licensed rituximab who relapsed could receive an additional infusion of 1,000 mg non-U.S.-licensed rituximab in combination with reintroduced or escalated prednisone dose. Maintenance and relapse infusions were administered no sooner than 16 weeks following the previous infusion.

The primary endpoint for the study was complete remission (complete epithelialization and absence of new and/or established lesions) at Month 24 without the use of prednisone therapy for 2 months or more (CRoff for greater than or equal to 2 months).

The results of the trial are presented in Table 18.

Table 18 Percentage of Pemphigus Patients in Complete Remission Off Corticosteroid Therapy for Two Months or More (CRoff greater than or equal to 2 months) at Month 24, PV Study 1 (Intent-to-Treat Population)
 | Non-U.S. licensed rituximab + short-term prednisone; N=46 | Prednisone; N=44
Number of responders; (response rate [%] | 41 (89%) | 15 (34%)
PV Patients | 34/38 (90%) | 10/36 (28%)
PF Patients | 7/8 (88%) | 5/8 (63%)

PV Study 2 (NCT02383589)

In a randomized, double-blind, double-dummy, active-comparator, multicenter study, the efficacy and safety of rituximab compared to mycophenolate mofetil (MMF) were evaluated in patients with moderate-to-severe PV receiving 60 to 120 mg/day oral prednisone or equivalent (1.0 to 1.5 mg/kg/day) at study entry and tapered to reach a dose of 60 or 80 mg/day by Day 1. Patients had a confirmed diagnosis of PV within the previous 24 months and evidence of moderate-to-severe disease defined as a total Pemphigus Disease Area Index (PDAI) activity score of greater than or equal to 15. The study consisted of a screening period of up to 28 days, a 52-week double-blind treatment period, and a 48-week safety follow up period.

One hundred and thirty-five patients were randomized to treatment with rituximab 1,000 mg administered on Day 1, Day 15, Week 24 and Week 26 or oral MMF 2 g/day (starting at 1 g/day on Day 1 and titrated to achieve a goal of 2 g/day by Week 2) for 52 weeks in combination with an initial dose of 60 or 80 mg oral prednisone with the aim of tapering to 0 mg/day by Week 24. Randomization was stratified by duration of PV (within the 1 year prior to screening or greater than 1 year) and geographical region. A dual-assessor approach was used during the study for efficacy and safety evaluations to prevent potential unblinding.

One hundred and twenty-five patients (excluding exploratory data from ten telemedicine patients) were analyzed for efficacy (Modified Intent-to-Treat Population). The primary efficacy endpoint for this study was the proportion of subjects achieving sustained complete remission defined as achieving healing of lesions with no new active lesions (i.e., PDAI activity score of 0) while on 0 mg/day prednisone or equivalent, and maintaining this response for at least 16 consecutive weeks, during the 52-week treatment period.

Secondary endpoints included cumulative oral corticosteroid dose and the total number of disease flares.

The results of the trial are presented in Table 19

Table 19 Percentage of PV Patients Who Achieved Sustained Complete Remission Off Corticosteroid Therapy for 16 Weeks or More at Week 52 (Modified Intent-to-Treat Population)
 | Rituximab; (N= 62) | MMF; (N = 63) | Difference (95% CI)
Numbers of responders; (response rate [%] | 25 (40.3%) | 6 (9.5%) | 30.80% (14.70%, 45.15%)
MMF = Mycophenolate mofetil. CI = Confidence Interval

Glucocorticoid exposure

The median (min, max) cumulative oral prednisone dose at Week 52 was 2,775 mg (450, 22,180) in the rituximab group compared to 4,005 mg (900, 19,920) in the MMF group. Topical corticosteroid use and pre-infusion IV methylprednisolone were not included in this analysis. Prior to each infusion, the rituximab group received IV methylprednisolone 100 mg and the MMF group received IV saline solution.

Disease flare

Disease flare was defined as an appearance of 3 or more new lesions a month that do not heal spontaneously within 1 week or by the extension of established lesions in a patient who has achieved disease control. The total number of disease flares was lower in patients treated with rituximab compared to MMF (6 vs. 44).

16 HOW SUPPLIED/STORAGE AND HANDLING

STORAGE AND HANDLING

TRUXIMA (rituximab-abbs) injection is a sterile, clear to opalescent, colorless to pale yellow, preservative-free solution for intravenous infusion supplied as a carton containing one 100 mg/10 mL (10 mg/mL) single-dose vial (NDC 63459-103-10) or a carton containing one 500 mg/50 mL (10 mg/mL) single-dose vial (NDC 63459-104-50).

Store TRUXIMA vials refrigerated at 2°C to 8°C (36°F to 46°F). TRUXIMA vials should be protected from direct sunlight. Do not freeze or shake.

17 PATIENT COUNSELING INFORMATION

Advise the patient to read the FDA-approved patient labeling (Medication Guide).

Infusion-Related Reactions

Inform patients about the signs and symptoms of infusion-related reactions. Advise patients to contact their healthcare provider immediately to report symptoms of infusion-related reactions including urticaria, hypotension, angioedema, sudden cough, breathing problems, weakness, dizziness, palpitations, or chest pain [see Warnings and Precautions (5.1)].

Severe Mucocutaneous Reactions

Advise patients to contact their healthcare provider immediately for symptoms of severe mucocutaneous reactions, including painful sores or ulcers on the mouth, blisters, peeling skin, rash, and pustules [see Warnings and Precautions (5.2)].

Hepatitis B Virus Reactivation

Advise patients to contact their healthcare provider immediately for symptoms of hepatitis including worsening fatigue or yellow discoloration of skin or eyes [see Warnings and Precautions (5.3)].

Progressive Multifocal Leukoencephalopathy (PML)

Advise patients to contact their healthcare provider immediately for signs and symptoms of PML, including new or changes in neurological symptoms such as confusion, dizziness or loss of balance, difficulty talking or walking, decreased strength or weakness on one side of the body, or vision problems [see Warnings and Precautions (5.4)].

Tumor Lysis Syndrome (TLS)

Advise patients to contact their healthcare provider immediately for signs and symptoms of tumor lysis syndrome such as nausea, vomiting, diarrhea, and lethargy [see Warnings and Precautions (5.5)].

Infections

Advise patients to contact their healthcare provider immediately for signs and symptoms of infections including fever, cold symptoms (e.g., rhinorrhea or laryngitis), flu symptoms (e.g., cough, fatigue, body aches), earache or headache, dysuria, oral herpes simplex infection, and painful wounds with erythema and advise patients of the increased risk of infections during and after treatment with TRUXIMA [see Warnings and Precautions (5.6)].

Cardiovascular Adverse Reactions

Advise patients of the risk of cardiovascular adverse reactions, including ventricular fibrillation, myocardial infarction, and cardiogenic shock. Advise patients to contact their healthcare provider immediately to report chest pain and irregular heartbeats [see Warnings and Precautions (5.7)].

Renal Toxicity

Advise patients of the risk of renal toxicity. Inform patients of the need for healthcare providers to monitor kidney function [see Warnings and Precautions (5.8)].

Bowel Obstruction and Perforation

Advise patients to contact their healthcare provider immediately for signs and symptoms of bowel obstruction and perforation, including severe abdominal pain or repeated vomiting [see Warnings and Precautions (5.9)].

Embryo-Fetal Toxicity

Advise pregnant women of the potential risk to a fetus. Advise females of reproductive potential to inform their healthcare provider of a known or suspected pregnancy [see Warnings and Precautions (5.11) and Use in Specific Populations (8.1)].

Advise females of reproductive potential to use effective contraception during treatment with TRUXIMA and for at least 12 months after the last dose [see Use in Specific Populations (8.3)].

Lactation

Advise women not to breastfeed during treatment with TRUXIMA and for at least 6 months after the last dose [see Use in Specific Populations (8.2)].

TRUXIMA® [rituximab-abbs]

TRUXIMA® is a registered trademark of CELLTRION, Inc

Manufactured by:

CELLTRION, Inc.

20, Academy-ro 51 beon-gil,

Yeonsu-gu, Incheon

22014, Republic of Korea

US License No. 1996

Marketed by:

Teva Pharmaceuticals USA, Inc.

North Wales, PA 19454

MEDICATION GUIDE
TRUXIMA®

(trux-ee'-mah)
(rituximab-abbs)
injection

What is the most important information I should know about TRUXIMA?
TRUXIMA can cause serious side effects that can lead to death, including:

- Infusion-related reactions. Infusion-related reactions are very common side effects of TRUXIMA treatment. Serious infusion-related reactions can happen during your infusion or within 24 hours after your infusion of TRUXIMA. Your healthcare provider should give you medicines before your infusion of TRUXIMA to decrease your chance of having a severe infusion-related reaction.
  Tell your healthcare provider or get medical help right away if you get any of these symptoms during or after an infusion of TRUXIMA:

- hives (red itchy welts) or rash
- itching
- swelling of your lips, tongue, throat or face
- sudden cough

- shortness of breath, difficulty breathing, or wheezing
- weakness
- dizziness or feel faint
- palpitations (feel like your heart is racing or fluttering)
- chest pain

- Severe skin and mouth reactions. Tell your healthcare provider or get medical help right away if you get any of these symptoms at any time during your treatment with TRUXIMA:
  - painful sores or ulcers on your skin, lips or in your mouth
  - blisters
  - peeling skin
  - rash
  - pustules
- Hepatitis B virus (HBV) reactivation. Before you receive your TRUXIMA treatment, your healthcare provider will do blood tests to check for HBV infection. If you have had hepatitis B or are a carrier of hepatitis B virus, receiving TRUXIMA could cause the virus to become an active infection again. Hepatitis B reactivation may cause serious liver problems including liver failure, and death. You should not receive TRUXIMA if you have active hepatitis B liver disease. Your healthcare provider will monitor you for hepatitis B infection during and for several months after you stop receiving TRUXIMA.
  Tell your healthcare provider right away if you get worsening tiredness, or yellowing of your skin or white part of your eyes, during treatment with TRUXIMA.
- Progressive Multifocal Leukoencephalopathy (PML). PML is a rare, serious brain infection caused by a virus that can happen in people who receive TRUXIMA. People with weakened immune systems can get PML. PML can result in death or severe disability. There is no known treatment, prevention, or cure for PML.
  Tell your healthcare provider right away if you have any new or worsening symptoms or if anyone close to you notices these symptoms:

- confusion
- dizziness or loss of balance
- difficulty walking or talking

- decreased strength or weakness on one side of your body
- vision problems

See "What are the possible side effects of TRUXIMA?" for more information about side effects.

What is TRUXIMA?
TRUXIMA is a prescription medicine used to treat:

- Adult with Non-Hodgkin's Lymphoma (NHL): alone or with other chemotherapy medicines.
- Chronic Lymphocytic Leukemia (CLL): with the chemotherapy medicines fludarabine and cyclophosphamide.
- Adults with Rheumatoid Arthritis (RA): with another prescription medicine called methotrexate, to reduce the signs and symptoms of moderate to severe active RA in adults, after treatment with at least one other medicine called a Tumor Necrosis Factor (TNF) antagonist has been used and did not work well enough.
- Adults with Granulomatosis with Polyangiitis (GPA) (Wegener’s Granulomatosis) and Microscopic Polyangiitis (MPA): with glucocorticoids, to treat GPA and MPA.

TRUIXMA is not indicated for treatment of children.

Before you receive TRUXIMA, tell your healthcare provider about all of your medical conditions, including if you:

- have had a severe reaction to TRUXIMA or a rituximab product
- have a history of heart problems, irregular heart beat or chest pain
- have lung or kidney problems
- have an infection or weakened immune system.
- have or have had any severe infections including:

- Hepatitis B virus (HBV)
- Hepatitis C virus (HCV)
- Cytomegalovirus (CMV)
- Herpes simplex virus (HSV)

- Parvovirus B19
- Varicella zoster virus (chickenpox or shingles)
- West Nile Virus

- have had a recent vaccination or are scheduled to receive vaccinations. You should not receive certain vaccines before or during treatment with TRUXIMA.
- are pregnant or plan to become pregnant. Talk to your healthcare provider about the risks to your unborn baby if you receive TRUXIMA during pregnancy.
  Females who are able to become pregnant should use effective birth control (contraception) during treatment with TRUXIMA and for at least 12 months after the last dose of TRUXIMA. Talk to your healthcare provider about effective birth control.
  Tell your healthcare provider right away if you become pregnant or think that you are pregnant during treatment with TRUXIMA.
- are breastfeeding or plan to breastfeed. It is not known if TRUXIMA passes into your breast milk. Do not breastfeed during treatment and for at least 6 months after your last dose of TRUXIMA.

Tell your healthcare provider about all the medicines you take, including prescription and over-the-counter medicines, vitamins, and herbal supplements. Especially tell your doctor if you take or have taken:

- a Tumor Necrosis Factor (TNF) inhibitor medicine
- a Disease Modifying Anti-Rheumatic Drug (DMARD)

If you are not sure if your medicine is one listed above, ask your healthcare provider.

How will I receive TRUXIMA?

- TRUXIMA is given by infusion through a needle placed in a vein (intravenous infusion), in your arm. Talk to your healthcare provider about how you will receive TRUXIMA.
- Your healthcare provider may prescribe medicines before each infusion of TRUXIMA to reduce infusion side effects such as fever and chills.
- Your healthcare provider should do blood tests regularly to check for side effects to TRUXIMA.
- Before each TRUXIMA treatment, your healthcare provider or nurse will ask you questions about your general health. Tell your healthcare provider or nurse about any new symptoms.

What are the possible side effects of TRUXIMA?
TRUXIMA can cause serious side effects, including:

- See "What is the most important information I should know about TRUXIMA?"
- Tumor Lysis Syndrome (TLS). TLS is caused by the fast breakdown of cancer cells. TLS can cause you to have:
  - kidney failure and the need for dialysis treatment
  - abnormal heart rhythm
  TLS can happen within 12 to 24 hours after an infusion of TRUXIMA. Your healthcare provider may do blood tests to check you for TLS. Your healthcare provider may give you medicine to help prevent TLS.
  Tell your healthcare provider right away if you have any of the following signs or symptoms of TLS:

- nausea
- vomiting

- diarrhea
- lack of energy

- Serious infections. Serious infections can happen during and after treatment with TRUXIMA, and can lead to death. TRUXIMA can increase your risk of getting infections and can lower the ability of your immune system to fight infections. Types of serious infections that can happen with TRUXIMA include bacterial, fungal, and viral infections. After receiving TRUXIMA, some people have developed low levels of certain antibodies in their blood for a long period of time (longer than 11 months). Some of these people with low antibody levels developed infections. People with serious infections should not receive TRUXIMA. Tell your healthcare provider right away if you have any symptoms of infection:
  - fever
  - cold symptoms, such as runny nose or sore throat that do not go away
  - flu symptoms, such as cough, tiredness, and body aches
  - earache or headache
  - pain during urination
  - cold sores in the mouth or throat
  - cuts, scrapes or incisions that are red, warm, swollen or painful
- Heart problems. TRUXIMA may cause chest pain, irregular heartbeats, and heart attack. Your healthcare provider may monitor your heart during and after treatment with TRUXIMA if you have symptoms of heart problems or have a history of heart problems. Tell your healthcare provider right away if you have chest pain or irregular heartbeats during treatment with TRUXIMA.
- Kidney problems, especially if you are receiving TRUXIMA for NHL. TRUXIMA can cause severe kidney problems that lead to death. Your healthcare provider should do blood tests to check how well your kidneys are working.
- Stomach and Serious bowel problems that can sometimes lead to death. Bowel problems, including blockage or tears in the bowel can happen if you receive TRUXIMA with chemotherapy medicines. Tell your healthcare provider right away if you have any severe stomach-area (abdomen) pain or repeated vomiting during treatment with TRUXIMA.

Your healthcare provider will stop treatment with TRUXIMA if you have severe, serious or life-threatening side effects.
The most common side effects of TRUXIMA include:

- infusion-related reactions (see "What is the most important information I should know about TRUXIMA?")
- infections (may include fever, chills)
- body aches
- tiredness
- nausea

In adult patients with GPA or MPA the most common side effects of TRUXIMA also include:

- low white and red blood cells
- swelling
- diarrhea
- muscle spasms

Other side effects with TRUXIMA include:

- aching joints during or within hours of receiving an infusion
- more frequent upper respiratory tract infection

These are not all of the possible side effects with TRUXIMA.
Call your doctor for medical advice about side effects. You may report side effects to FDA at 1-800-FDA-1088.

General information about the safe and effective use of TRUXIMA.
Medicines are sometimes prescribed for purposes other than those listed in a Medication Guide. You can ask your pharmacist or healthcare provider for information about TRUXIMA that is written for healthcare professionals.

What are the ingredients in TRUXIMA?
Active ingredient: rituximab-abbs
Inactive ingredients: polysorbate 80, sodium chloride, tri-sodium citrate dihydrate, and Water for Injection, USP.

Manufactured by: CELLTRION, Inc. 20, Academy-ro 51 beon-gil, Yeonsu-gu, Incheon, 22014 Republic of Korea

US License Number 1996

Marketed by: Teva Pharmaceuticals USA, Inc. North Wales, PA 19454

For more information, go to www.TRUXIMA.com or call 1-888-483-8279.

This Medication Guide has been approved by the U.S. Food and Drug Administration

Revised: 03/2020

PRINCIPAL DISPLAY PANEL - 100mg Vial Carton

NDC 63459-103-10 Truxima® (rituximiab-abbs) Injection
100 mg/10 mL(10 mg/mL)
For Intravenous Use after Dilution
One single-dose vial.
Discard unused portion.
ATTENTION PHARMACIST:
PROVIDE ENCLOSED MEDICATION GUIDE TO PATIENT.

Rx only teva

PRINCIPAL DISPLAY PANEL - 500 mg Vial Carton

NDC 63459-104-50 Truxima® (rituximiab-abbs) Injection

500 mg/50 mL (10 mg/mL)

For Intravenous Use after Dilution One single-dose vial.

Discard unused portion. ATTENTION PHARMACIST:

PROVIDE ENCLOSED MEDICATION GUIDE TO PATIENT.

Rx only teva